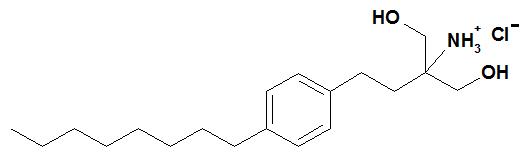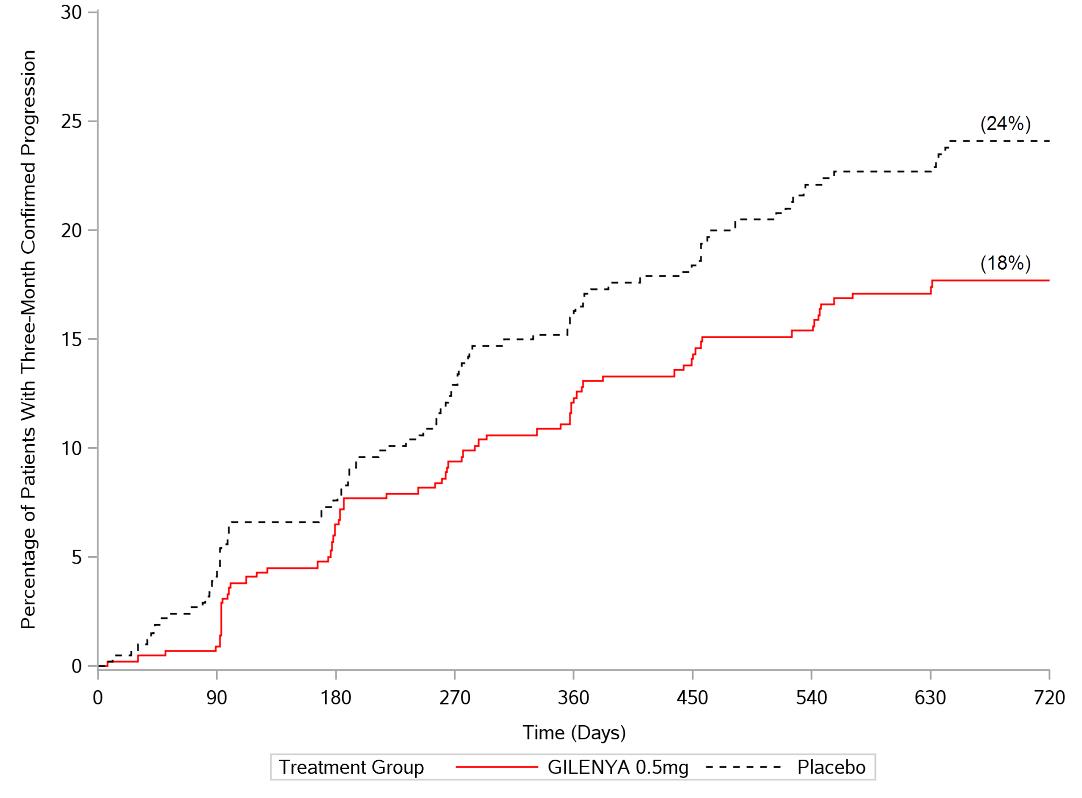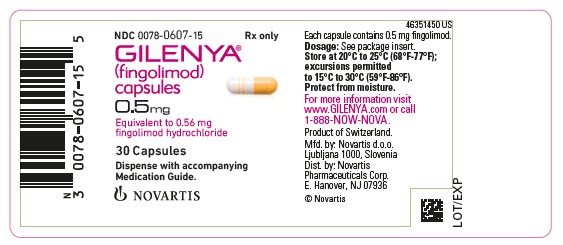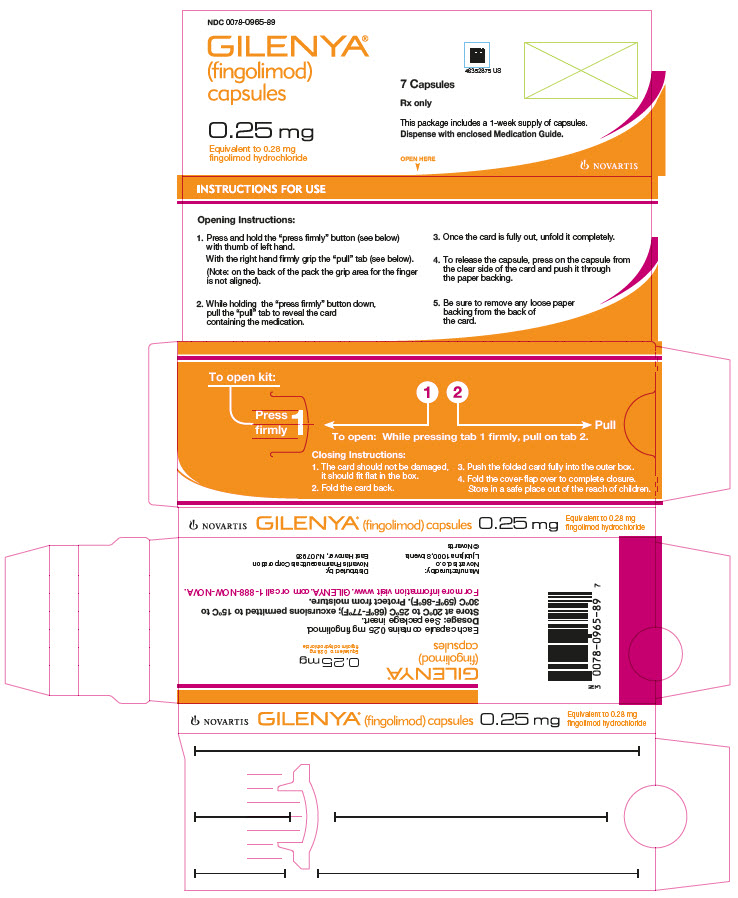 DRUG LABEL: Gilenya
NDC: 0078-0607 | Form: CAPSULE
Manufacturer: Novartis Pharmaceuticals Corporation
Category: prescription | Type: HUMAN PRESCRIPTION DRUG LABEL
Date: 20250822

ACTIVE INGREDIENTS: FINGOLIMOD HYDROCHLORIDE 0.5 mg/1 1
INACTIVE INGREDIENTS: GELATIN; MAGNESIUM STEARATE; MANNITOL; TITANIUM DIOXIDE; FERRIC OXIDE YELLOW

HIGHLIGHTS OF PRESCRIBING INFORMATION

These highlights do not include all the information needed to use GILENYA® safely and effectively.
See full prescribing information for GILENYA.
GILENYA (fingolimod) capsules, for oral use
Initial U.S. Approval: 2010

RECENT MAJOR CHANGES

Warnings and Precautions (5.8, 5.11) | 8/2025

1 INDICATIONS AND USAGE

GILENYA is a sphingosine 1-phosphate receptor modulator indicated for the treatment of relapsing forms of multiple sclerosis (MS), to include clinically isolated syndrome, relapsing-remitting disease, and active secondary progressive disease, in patients 10 years of age and older. (1)

2 DOSAGE AND ADMINISTRATION

- Assessments are required prior to initiating GILENYA. (2.1)
- Recommended dosage for adults and pediatric patients (10 years of age and older) weighing more than 40 kg: 0.5 mg orally once daily, with or without food. (2.2, 2.3)
- Recommended dosage for pediatric patients (10 years of age and above) weighing less than or equal to 40 kg: 0.25 mg orally once daily, with or without food. (2.2, 2.3)
- First-Dose Monitoring (including reinitiation after discontinuation greater than 14 days and dose increases):
  - Observe all patients for bradycardia for at least 6 hours; monitor pulse and blood pressure hourly. Electrocardiograms (ECGs) prior to dosing and at end of observation period required. (2.4)
  - Monitor until resolution if heart rate < 45 beats per minute (bpm) in adults, < 55 bpm in patients aged 12 years and above, or < 60 bpm in pediatric patients aged 10 to below 12 years, atrioventricular (AV) block, or if lowest postdose heart rate is at the end of the observation period. (2.4)
  - Monitor symptomatic bradycardia with ECG until resolved. Continue overnight if intervention is required; repeat first-dose monitoring for second dose. (2.4)
  - Observe patients overnight if at higher risk of symptomatic bradycardia, heart block, prolonged QTc interval, or if taking drugs with known risk of torsades de pointes. (2.4, 7.1)

3 DOSAGE FORMS AND STRENGTHS

0.25 mg hard capsules (3)

0.5 mg hard capsules (3)

4 CONTRAINDICATIONS

- Recent myocardial infarction, unstable angina, stroke, transient ischemic attack (TIA), decompensated heart failure with hospitalization, or Class III/IV heart failure. (4)
- History of Mobitz Type II 2nd degree or 3rd degree AV block or sick sinus syndrome, unless patient has a pacemaker. (4)
- Baseline QTc interval ≥ 500 msec. (4)
- Cardiac arrhythmias requiring anti-arrhythmic treatment with Class Ia or Class III anti-arrhythmic drugs. (4)
- Hypersensitivity to fingolimod or its excipients. (4)

5 WARNINGS AND PRECAUTIONS

- Infections: GILENYA may increase the risk. Obtain a complete blood count (CBC) before initiating treatment. Monitor for infection during treatment and for 2 months after discontinuation. Do not start in patients with active infections. (5.2)
- Progressive Multifocal Leukoencephalopathy (PML): Withhold GILENYA at the first sign or symptom suggestive of PML. (5.3)
- Macular Edema: Increases the risk of macular edema. Obtain a baseline evaluation of the fundus, including the macula, near the start of treatment with GILENYA. Conduct an evaluation of the fundus, including the macula, 3 to 4 months after treatment start, periodically while on therapy and any time there is a change in vision. Consider discontinuing GILENYA if macular edema develops. Diabetes mellitus and uveitis increase the risk. (5.4)
- Liver Injury: Obtain liver enzyme results before initiation and periodically during treatment. Closely monitor patients with severe hepatic impairment. Discontinue if there is evidence of liver injury without other cause. (5.5, 8.6, 12.3)
- Posterior Reversible Encephalopathy Syndrome (PRES): If suspected, discontinue GILENYA. (5.6)
- Respiratory Effects: Evaluate when clinically indicated. (5.7)
- Fetal Risk: May cause fetal harm. Advise females of reproductive potential of the potential risk to a fetus and to use an effective method of contraception during treatment and for 2 months after stopping GILENYA. (5.8, 8.1, 8.3)
- Severe Increase in Disability After Stopping GILENYA: Monitor for development of severe increase in disability following discontinuation and begin appropriate treatment as needed. (5.9)
- Tumefactive MS: Consider when severe MS relapse occurs during treatment or after discontinuation. Obtain imaging and begin treatment as needed. (5.10)
- Increased Blood Pressure (BP): Monitor BP in adult and pediatric patients during treatment. (5.11)
- Malignancies: Skin examination prior to or shortly after the start of treatment and periodically thereafter is recommended. Suspicious skin lesions should be evaluated. (5.12)

6 ADVERSE REACTIONS

Most common adverse reactions (incidence ≥ 10% and greater than placebo): Headache, liver transaminase elevation, diarrhea, cough, influenza, sinusitis, back pain, abdominal pain, and pain in extremity. (6.1)

To report SUSPECTED ADVERSE REACTIONS, contact Novartis Pharmaceuticals Corporation at 1-888-669-6682 or FDA at 1-800-FDA-1088 or www.fda.gov/medwatch.

7 DRUG INTERACTIONS

- Systemic Ketoconazole: Monitor during concomitant use. (7.2, 12.3)
- Vaccines: Avoid live attenuated vaccines during, and for 2 months after stopping GILENYA treatment. (5.2, 7.3)

FULL PRESCRIBING INFORMATION

1 INDICATIONS AND USAGE

GILENYA is indicated for the treatment of relapsing forms of multiple sclerosis (MS), to include clinically isolated syndrome, relapsing-remitting disease, and active secondary progressive disease, in patients 10 years of age and older.

2 DOSAGE AND ADMINISTRATION

2.1 Assessment Prior to Initiating GILENYA

Cardiac Evaluation

Obtain a cardiac evaluation in patients with certain preexisting conditions [see Warnings and Precautions (5.1)].

Prior to starting treatment, determine whether patients are taking drugs that could slow heart rate or atrioventricular (AV) conduction [see Dosage and Administration (2.4), Drug Interactions (7.5)].

Complete Blood Count (CBC)

Review results of a recent CBC [see Warnings and Precautions (5.2), Drug Interactions (7.6)].

Serum Transaminases (ALT and AST) and Total Bilirubin Levels

Prior to starting treatment with GILENYA (i.e., within 6 months), obtain serum transaminases [alanine transaminase (ALT) and aspartate transferase (AST)] and total bilirubin levels [see Warnings and Precautions (5.5)].

Ophthalmic Assessment

Obtain a baseline evaluation of the fundus, including the macula, near the start of the treatment with GILENYA [see Warnings and Precautions (5.4)].

Skin Examination

Obtain a baseline skin examination prior to or shortly after initiation of GILENYA. If a suspicious skin lesion is observed, it should be promptly evaluated [see Warnings and Precautions (5.12)].

Prior Medications

If patients are taking antineoplastic, immunosuppressive, or immune-modulating therapies, or if there is a history of prior use of these drugs, consider possible unintended additive immunosuppressive effects before initiating treatment with GILENYA [see Warnings and Precautions (5.2), Drug Interactions (7.4)].

Vaccinations

Test patients for antibodies to varicella zoster virus (VZV) before initiating GILENYA; VZV vaccination of antibody-negative patients is recommended prior to commencing treatment with GILENYA [see Warnings and Precautions (5.2)]. It is recommended that pediatric patients if possible, complete all immunizations in accordance with current immunization guidelines prior to initiating GILENYA therapy.

2.2 Important Administration Instructions

Patients who initiate GILENYA, and those who reinitiate treatment after discontinuation for longer than 14 days, require first-dose monitoring. This monitoring is also recommended when the dose is increased in pediatric patients [see Dosage and Administration (2.4, 2.5)].

GILENYA can be taken with or without food.

2.3 Recommended Dosage

In adults and pediatric patients 10 years of age and older weighing more than 40 kg, the recommended dosage of GILENYA is 0.5 mg orally once daily.

In pediatric patients 10 years of age and older weighing less than or equal to 40 kg, the recommended dosage of GILENYA is 0.25 mg orally once daily.

Fingolimod doses higher than 0.5 mg are associated with a greater incidence of adverse reactions without additional benefit.

2.4 First-Dose Monitoring

Initiation of GILENYA treatment results in a decrease in heart rate, for which monitoring is recommended [see Warnings and Precautions (5.1), Clinical Pharmacology (12.2)]. Prior to dosing and at the end of the observation period, obtain an electrocardiogram (ECG) in all patients.

First 6-Hour Monitoring

Administer the first dose of GILENYA in a setting in which resources to appropriately manage symptomatic bradycardia are available. Monitor all patients for 6 hours after the first dose for signs and symptoms of bradycardia with hourly pulse and blood pressure measurement.

Additional Monitoring After 6-Hour Monitoring

Continue monitoring until the abnormality resolves if any of the following is present (even in the absence of symptoms) after 6 hours:

- the heart rate 6 hours postdose is less than 45 beats per minute (bpm) in adults, less than 55 bpm in pediatric patients 12 years of age and older, or less than 60 bpm in pediatric patients 10 or 11 years of age;
- the heart rate 6 hours postdose is at the lowest value postdose suggesting that the maximum pharmacodynamic effect on the heart may not have occurred;
- the ECG 6 hours postdose shows new onset second degree or higher atrioventricular (AV) block.

If postdose symptomatic bradycardia occurs, initiate appropriate management, begin continuous ECG monitoring, and continue monitoring until the symptoms have resolved if no pharmacological treatment is required. If pharmacological treatment is required, continue monitoring overnight and repeat 6-hour monitoring after the second dose.

Overnight Monitoring

Continuous overnight ECG monitoring in a medical facility should be instituted:

- in patients that require pharmacologic intervention for symptomatic bradycardia. In these patients, the first-dose monitoring strategy should be repeated after the second dose of GILENYA;
- in patients with some preexisting heart and cerebrovascular conditions [see Warnings and Precautions (5.1)];
- in patients with a prolonged QTc interval before dosing or during 6-hour observation, or at additional risk for QT prolongation, or on concurrent therapy with QT prolonging drugs with a known risk of torsades de pointes [see Warnings and Precautions (5.1), Drug Interactions (7.1)];
- in patients receiving concurrent therapy with drugs that slow heart rate or AV conduction [see Drug Interactions (7.5)].

2.5 Monitoring After Reinitiation of Therapy Following Discontinuation

When restarting GILENYA after discontinuation for more than 14 days after the first month of treatment, perform first-dose monitoring, because effects on heart rate and AV conduction may recur on reintroduction of GILENYA treatment [see Dosage and Administration (2.4)]. The same precautions (first-dose monitoring) as for initial dosing are applicable. Within the first 2 weeks of treatment, first-dose procedures are recommended after interruption of 1 day or more; during Weeks 3 and 4 of treatment, first-dose procedures are recommended after treatment interruption of more than 7 days.

3 DOSAGE FORMS AND STRENGTHS

GILENYA is available as:

- 0.25 mg hard capsules with an ivory opaque body and cap, with black radial imprint “FTY 0.25 mg” on the cap and a black radial band on the capsule body.
- 0.5 mg hard capsules with a white opaque body and bright yellow cap imprinted with “FTY 0.5 mg” on the cap and 2 radial bands imprinted on the capsule body with yellow ink.

4 CONTRAINDICATIONS

GILENYA is contraindicated in patients who have:

- in the last 6 months experienced myocardial infarction, unstable angina, stroke, transient ischemic attack (TIA), decompensated heart failure requiring hospitalization or Class III/IV heart failure
- a history or presence of Mobitz Type II second-degree or third-degree AV block or sick sinus syndrome, unless patient has a functioning pacemaker [see Warnings and Precautions (5.1)]
- a baseline QTc interval ≥ 500 msec
- cardiac arrhythmias requiring anti-arrhythmic treatment with Class Ia or Class III anti-arrhythmic drugs
- had a hypersensitivity reaction to fingolimod or any of the excipients in GILENYA. Observed reactions include rash, urticaria and angioedema upon treatment initiation [see Warnings and Precautions (5.14)].

5 WARNINGS AND PRECAUTIONS

5.1 Bradyarrhythmia and Atrioventricular Blocks

Because of a risk for bradyarrhythmia and AV blocks, patients should be monitored during GILENYA treatment initiation [see Dosage and Administration (2.4)].

Reduction in Heart Rate

After the first dose of GILENYA, the heart rate decrease starts within an hour. On Day 1, the maximum decline in heart rate generally occurs within 6 hours and recovers, although not to baseline levels, by 8 to 10 hours postdose. Because of physiological diurnal variation, there is a second period of heart rate decrease within 24 hours after the first dose. In some patients, heart rate decrease during the second period is more pronounced than the decrease observed in the first 6 hours. Heart rates below 40 bpm in adults, and below 50 bpm in pediatric patients occurred rarely. In controlled clinical trials in adult patients, adverse reactions of symptomatic bradycardia following the first dose were reported in 0.6% of patients receiving GILENYA 0.5 mg and in 0.1% of patients on placebo. Patients who experienced bradycardia were generally asymptomatic, but some patients experienced hypotension, dizziness, fatigue, palpitations, and/or chest pain that usually resolved within the first 24 hours on treatment.

Patients with some preexisting conditions (e.g., ischemic heart disease, history of myocardial infarction, congestive heart failure, history of cardiac arrest, cerebrovascular disease, uncontrolled hypertension, history of symptomatic bradycardia, history of recurrent syncope, severe untreated sleep apnea, AV block, sinoatrial heart block) may poorly tolerate the GILENYA-induced bradycardia, or experience serious rhythm disturbances after the first dose of GILENYA. Prior to treatment with GILENYA, these patients should have a cardiac evaluation by a physician appropriately trained to conduct such evaluation, and if treated with GILENYA, should be monitored overnight with continuous ECG in a medical facility after the first dose.

Since initiation of GILENYA treatment results in decreased heart rate and may prolong the QT interval, patients with a prolonged QTc interval (> 450 msec adult and pediatric males, > 470 msec adult females, or > 460 msec pediatric females) before dosing or during 6-hour observation, or at additional risk for QT prolongation (e.g., hypokalemia, hypomagnesemia, congenital long-QT syndrome), or on concurrent therapy with QT prolonging drugs with a known risk of torsades de pointes (e.g., citalopram, chlorpromazine, haloperidol, methadone, erythromycin) should be monitored overnight with continuous ECG in a medical facility.

Following the second dose, a further decrease in heart rate may occur when compared to the heart rate prior to the second dose, but this change is of a smaller magnitude than that observed following the first dose. With continued dosing, the heart rate returns to baseline within 1 month of chronic treatment. Clinical data indicate effects of GILENYA on heart rate are maximal after the first dose although milder effects on heart rate may persist for, on average, 2 to 4 weeks after initiation of therapy at which time heart rate generally returns to baseline. Physicians should continue to be alert to patient reports of cardiac symptoms.

Atrioventricular Blocks

Initiation of GILENYA treatment has resulted in transient AV conduction delays. In controlled clinical trials in adult patients, first-degree AV block after the first dose occurred in 4.7% of patients receiving GILENYA and 1.6% of patients on placebo. In a study of 697 patients with available 24-hour Holter monitoring data after their first dose (N = 351 receiving GILENYA and N = 346 on placebo), second-degree AV blocks (Mobitz Types I [Wenckebach] or 2:1 AV blocks) occurred in 4% (N = 14) of patients receiving GILENYA and 2% (N = 7) of patients on placebo. Of the 14 patients receiving GILENYA, 7 patients had 2:1 AV block (5 patients within the first 6 hours postdose and 2 patients after 6 hours postdose). All second-degree AV blocks on placebo were Mobitz Type I and occurred after the first 12 hours postdose. The conduction abnormalities were usually transient and asymptomatic, and resolved within the first 24 hours on treatment, but they occasionally required treatment with atropine or isoproterenol.

Postmarketing Experience

In the postmarketing setting, third-degree AV block and AV block with junctional escape have been observed during the first-dose 6-hour observation period with GILENYA. Isolated delayed onset events, including transient asystole and unexplained death, have occurred within 24 hours of the first dose. These events were confounded by concomitant medications and/or preexisting disease, and the relationship to GILENYA is uncertain. Cases of syncope were also reported after the first dose of GILENYA.

5.2 Infections

Risk of Infections

GILENYA causes a dose-dependent reduction in peripheral lymphocyte count to 20%–30% of baseline values because of reversible sequestration of lymphocytes in lymphoid tissues. GILENYA may therefore increase the risk of infections, some serious in nature [see Clinical Pharmacology (12.2)]. Life-threatening and fatal infections have occurred in association with GILENYA.

Before initiating treatment with GILENYA, a recent CBC (i.e., within 6 months or after discontinuation of prior therapy) should be available. Consider suspending treatment with GILENYA if a patient develops a serious infection, and reassess the benefits and risks prior to reinitiation of therapy. Because the elimination of fingolimod after discontinuation may take up to 2 months, continue monitoring for infections throughout this period. Instruct patients receiving GILENYA to report symptoms of infections to a physician. Patients with active acute or chronic infections should not start treatment until the infection(s) is resolved.

In MS placebo-controlled trials in adult patients, the overall rate of infections (72%) with GILENYA was similar to placebo. However, bronchitis, herpes zoster, influenza, sinusitis, and pneumonia were more common in GILENYA-treated patients. Serious infections occurred at a rate of 2.3% in the GILENYA group versus 1.6% in the placebo group.

In the postmarketing setting, serious infections with opportunistic pathogens, including viruses (e.g., John Cunningham virus [JCV], herpes simplex viruses 1 and 2, varicella zoster virus), fungi (e.g., cryptococci), and bacteria (e.g., atypical mycobacteria) have been reported with GILENYA. Patients with symptoms and signs consistent with any of these infections should undergo prompt diagnostic evaluation and appropriate treatment.

Herpes Viral Infections

In placebo-controlled trials in adult patients, the rate of herpetic infections was 9% in patients receiving GILENYA 0.5 mg and 7% on placebo.

Two patients died of herpetic infections during controlled trials. One death was due to disseminated primary herpes zoster and the other was to herpes simplex encephalitis. In both cases, the patients were taking a 1.25 mg dose of fingolimod (higher than the recommended 0.5 mg dose) and had received high-dose corticosteroid therapy to treat suspected MS relapses.

Serious, life-threatening events of disseminated varicella zoster and herpes simplex infections, including cases of encephalitis and multiorgan failure, have occurred with GILENYA in the postmarketing setting. Include disseminated herpetic infections in the differential diagnosis of patients who are receiving GILENYA and present with an atypical MS relapse or multiorgan failure.

Cases of Kaposi’s sarcoma have been reported in the postmarketing setting. Kaposi’s sarcoma is an angioproliferative disorder that is associated with infection with human herpes virus 8 (HHV-8). Patients with symptoms or signs consistent with Kaposi’s sarcoma should be referred for prompt diagnostic evaluation and management.

Cryptococcal Infections

Cryptococcal infections, including cases of fatal cryptococcal meningitis and disseminated cryptococcal infections, have been reported with GILENYA in the postmarketing setting. Cryptococcal infections have generally occurred after approximately 2 years of GILENYA treatment, but may occur earlier. The relationship between the risk of cryptococcal infection and the duration of treatment is unknown. Patients with symptoms and signs consistent with a cryptococcal infection should undergo prompt diagnostic evaluation and treatment.

Prior and Concomitant Treatment with Antineoplastic, Immunosuppressive, or Immune-Modulating Therapies

In clinical studies, patients who received GILENYA did not receive concomitant treatment with antineoplastic, non-corticosteroid immunosuppressive, or immune-modulating therapies used for treatment of MS. Concomitant use of GILENYA with any of these therapies, and also with corticosteroids, would be expected to increase the risk of immunosuppression [see Drug Interactions (7.4)].

When switching to GILENYA from immune-modulating or immunosuppressive medications, consider the duration of their effects and their mode of action to avoid unintended additive immunosuppressive effects.

Varicella Zoster Virus Antibody Testing/Vaccination

Patients without a healthcare professional confirmed history of chickenpox or without documentation of a full course of vaccination against VZV should be tested for antibodies to VZV before initiating GILENYA. VZV vaccination of antibody-negative patients is recommended prior to commencing treatment with GILENYA, following which initiation of treatment with GILENYA should be postponed for 1 month to allow the full effect of vaccination to occur [see Drug Interactions (7.3), Use in Specific Populations (8.4)].

Human Papilloma Virus Infection

Human papilloma virus (HPV) infections, including papilloma, dysplasia, warts, and HPV-related cancer, have been reported in patients treated with GILENYA in the postmarketing setting. Vaccination against HPV should be considered prior to treatment initiation with GILENYA, taking into account vaccination recommendations. Cancer screening, including Papanicolaou (Pap) test, is recommended as per standard of care for patients using an immunosuppressive therapy.

5.3 Progressive Multifocal Leukoencephalopathy

Cases of progressive multifocal leukoencephalopathy (PML) have occurred in patients with MS who received GILENYA in the postmarketing setting. PML is an opportunistic viral infection of the brain caused by the JC virus (JCV) that typically only occurs in patients who are immunocompromised, and that usually leads to death or severe disability. PML has occurred in patients who had not been treated previously with natalizumab, which has a known association with PML, were not taking any other immunosuppressive or immunomodulatory medications concomitantly, and did not have any ongoing systemic medical conditions resulting in compromised immune system function. Longer treatment duration increases the risk of PML in GILENYA-treated patients; the majority of cases have occurred in patients treated with GILENYA for at least 18 months.

At the first sign or symptom suggestive of PML, withhold GILENYA and perform an appropriate diagnostic evaluation. Typical symptoms associated with PML are diverse, progress over days to weeks, and include progressive weakness on one side of the body or clumsiness of limbs, disturbance of vision, and changes in thinking, memory, and orientation leading to confusion and personality changes.

Magnetic resonance imaging (MRI) findings may be apparent before clinical signs or symptoms. Cases of PML, diagnosed based on MRI findings and the detection of JCV DNA in the cerebrospinal fluid in the absence of clinical signs or symptoms specific to PML, have been reported in patients treated with MS medications associated with PML, including GILENYA. Many of these patients subsequently became symptomatic with PML. Therefore, monitoring with MRI for signs that may be consistent with PML may be useful, and any suspicious findings should lead to further investigation to allow for an early diagnosis of PML, if present. Lower PML-related mortality and morbidity have been reported following discontinuation of another MS medication associated with PML in patients with PML who were initially asymptomatic compared to patients with PML who had characteristic clinical signs and symptoms at diagnosis. It is not known whether these differences are due to early detection and discontinuation of MS treatment or due to differences in disease in these patients.

If PML is confirmed, treatment with GILENYA should be discontinued.

Immune reconstitution inflammatory syndrome (IRIS) has been reported in patients treated with S1P receptor modulators, including GILENYA, who developed PML and subsequently discontinued treatment. IRIS presents as a clinical decline in the patient’s condition that may be rapid, can lead to serious neurological complications or death, and is often associated with characteristic changes on MRI. The time to onset of IRIS in patients with PML was generally within a few months after S1P receptor modulator discontinuation. Monitoring for development of IRIS and appropriate treatment of the associated inflammation should be undertaken.

5.4 Macular Edema

S1P receptor modulators, including GILENYA, have been associated with an increased risk of macular edema. Obtain a baseline evaluation of the fundus, including the macula, near the start of treatment with GILENYA. Perform an examination of the fundus, including the macula, 3 to 4 months after starting treatment, periodically while on therapy, and any time there is a change in vision.

A dose-dependent increase in the risk of macular edema occurred in the GILENYA clinical development program.

In 2-year double-blind, placebo-controlled studies in adult patients with multiple sclerosis, macular edema with or without visual symptoms occurred in 1.5% of patients (11/799) treated with fingolimod 1.25 mg, 0.5% of patients (4/783) treated with GILENYA 0.5 mg, and 0.4% of patients (3/773) treated with placebo. Macular edema occurred predominantly during the first 3 to 4 months of therapy. These clinical trials excluded patients with diabetes mellitus, a known risk factor for macular edema (see below Macular Edema in Patients with History of Uveitis or Diabetes Mellitus). Symptoms of macular edema included blurred vision and decreased visual acuity. Routine ophthalmological examination detected macular edema in some patients with no visual symptoms. Macular edema generally partially or completely resolved with or without treatment after drug discontinuation. Some patients had residual visual acuity loss even after resolution of macular edema. Macular edema has also been reported in patients taking GILENYA in the postmarketing setting, usually within the first 6 months of treatment.

Continuation of GILENYA in patients who develop macular edema has not been evaluated. Macular edema over an extended period of time (i.e., 6 months) can lead to permanent visual loss. Consider discontinuing GILENYA if macular edema develops; this decision should include an assessment of the potential benefits and risks for the individual patient. The risk of recurrence after rechallenge has not been evaluated.

Macular Edema in Patients with History of Uveitis or Diabetes Mellitus

Patients with a history of uveitis and patients with diabetes mellitus are at increased risk of macular edema during GILENYA therapy. In the combined clinical trial experience in adult patients with all doses of fingolimod, the rate of macular edema was higher in MS patients with a history of uveitis compared to those without a history of uveitis (approximately 20% versus 0.6%, respectively). GILENYA has not been tested in MS patients with diabetes mellitus.

5.5 Liver Injury

Clinically significant liver injury has occurred in patients treated with GILENYA in the postmarketing setting. Signs of liver injury, including markedly elevated serum hepatic enzymes and elevated total bilirubin, have occurred as early as ten days after the first dose and have also been reported after prolonged use. Cases of acute liver failure requiring liver transplant have been reported.

In 2-year placebo-controlled clinical trials in adult patients, elevation of liver enzymes (ALT, AST, and GGT) to 3-fold the upper limit of normal (ULN) or greater occurred in 14% of patients treated with GILENYA 0.5 mg and 3% of patients on placebo. Elevations 5-fold the ULN or greater occurred in 4.5% of patients on GILENYA and 1% of patients on placebo. The majority of elevations occurred within 6 to 9 months. In clinical trials, GILENYA was discontinued if the elevation exceeded 5 times the ULN. Serum transaminase levels returned to normal within approximately 2 months after discontinuation of GILENYA. Recurrence of liver transaminase elevations occurred with rechallenge in some patients.

Prior to starting treatment with GILENYA (within 6 months), obtain serum transaminases (ALT and AST) and total bilirubin levels. Obtain transaminase levels and total bilirubin levels periodically until two months after GILENYA discontinuation.

Patients should be monitored for signs and symptoms of any hepatic injury. Measure liver transaminase and bilirubin levels promptly in patients who report symptoms that may indicate liver injury, including new or worsening fatigue, anorexia, right upper abdominal discomfort, dark urine, or jaundice. In this clinical context, if the patient is found to have an alanine aminotransferase (ALT) greater than three times the reference range with serum total bilirubin greater than two times the reference range, treatment with GILENYA should be interrupted. Treatment should not be resumed if a plausible alternative etiology for the signs and symptoms cannot be established, because these patients are at risk for severe drug-induced liver injury.

Because GILENYA exposure is doubled in patients with severe hepatic impairment, these patients should be closely monitored, as the risk of adverse reactions is greater [see Use in Specific Populations (8.6), Clinical Pharmacology (12.3)].

5.6 Posterior Reversible Encephalopathy Syndrome

There have been rare cases of posterior reversible encephalopathy syndrome (PRES) reported in adult patients receiving GILENYA. Symptoms reported included sudden onset of severe headache, altered mental status, visual disturbances, and seizure. Symptoms of PRES are usually reversible but may evolve into ischemic stroke or cerebral hemorrhage. Delay in diagnosis and treatment may lead to permanent neurological sequelae. If PRES is suspected, GILENYA should be discontinued.

5.7 Respiratory Effects

Dose-dependent reductions in forced expiratory volume over 1 second (FEV1) and diffusion lung capacity for carbon monoxide (DLCO) were observed in patients treated with GILENYA as early as 1 month after treatment initiation. In 2-year placebo-controlled trials in adult patients, the reduction from baseline in the percent of predicted values for FEV1 at the time of last assessment on drug was 2.8% for GILENYA 0.5 mg and 1.0% for placebo. For DLCO, the reduction from baseline in percent of predicted values at the time of last assessment on drug was 3.3% for GILENYA 0.5 mg and 0.5% for placebo. The changes in FEV1 appear to be reversible after treatment discontinuation. There is insufficient information to determine the reversibility of the decrease of DLCO after drug discontinuation. In MS placebo-controlled trials in adult patients, dyspnea was reported in 9% of patients receiving GILENYA 0.5 mg and 7% of patients receiving placebo. Several patients discontinued GILENYA because of unexplained dyspnea during the extension (uncontrolled) studies. GILENYA has not been tested in MS patients with compromised respiratory function.

Spirometric evaluation of respiratory function and evaluation of DLCO should be performed during therapy with GILENYA if clinically indicated.

5.8 Fetal Risk

GILENYA may cause fetal harm when administered to a pregnant woman.

In animal reproduction studies conducted in rats and rabbits, developmental toxicity was observed with administration of fingolimod at doses less than the recommended human dose.

Available observational pregnancy registry data suggest that use of GILENYA is associated with an increased prevalence of major birth defects in comparison to the general population.

Advise pregnant women and females of reproductive potential of the potential risk to a fetus. Because it takes approximately 2 months to eliminate GILENYA from the body, advise females of reproductive potential to use effective contraception to avoid pregnancy during and for 2 months after stopping GILENYA treatment [see Use in Specific Populations (8.1, 8.3)].

5.9 Severe Increase in Disability After Stopping GILENYA

Severe increase in disability accompanied by multiple new lesions on MRI has been reported after discontinuation of GILENYA in the postmarketing setting. Patients in most of these reported cases did not return to the functional status they had before stopping GILENYA. The increase in disability generally occurred within 12 weeks after stopping GILENYA, but was reported up to 24 weeks after GILENYA discontinuation.

Monitor patients for development of severe increase in disability following discontinuation of GILENYA and begin appropriate treatment as needed.

After stopping GILENYA in the setting of PML, monitor for development of immune reconstitution inflammatory syndrome (PML-IRIS) [see Warnings and Precautions (5.3)].

5.10 Tumefactive Multiple Sclerosis

MS relapses with tumefactive demyelinating lesions on imaging have been observed during GILENYA therapy and after GILENYA discontinuation in the postmarketing setting. Most reported cases of tumefactive MS in patients receiving GILENYA have occurred within the first 9 months after GILENYA initiation, but tumefactive MS may occur at any point during treatment. Cases of tumefactive MS have also been reported within the first 4 months after GILENYA discontinuation. Tumefactive MS should be considered when a severe MS relapse occurs during GILENYA treatment, especially during initiation, or after discontinuation of GILENYA, prompting imaging evaluation and initiation of appropriate treatment.

5.11 Increased Blood Pressure

Increases in blood pressure have been observed in patients treated with GILENYA.

In adult MS controlled clinical trials, patients treated with GILENYA 0.5 mg had an average increase over placebo of approximately 3 mmHg in systolic pressure, and approximately 2 mmHg in diastolic pressure, first detected after approximately 1 month of treatment initiation, and persisting with continued treatment. Hypertension was reported as an adverse reaction in 8% of patients on GILENYA 0.5 mg and in 4% of patients on placebo.

Monitor blood pressure (BP) in adult and pediatric patients during treatment with GILENYA.

5.12 Malignancies

Cutaneous Malignancies

The risk of cutaneous malignancies (including basal cell carcinoma (BCC), squamous cell carcinoma (SCC) and melanoma) is increased in patients treated with S1P receptor modulators. Use of GILENYA has been associated with an increased risk of BCC and melanoma.

In two-year placebo-controlled trials in adult patients, the incidence of BCC was 2% in patients on GILENYA 0.5 mg and 1% in patients on placebo [see Adverse Reactions (6.1)]. Melanoma, basal cell carcinoma, squamous cell carcinoma, Kaposi’s sarcoma [see Warnings and Precautions (5.2)], and Merkel cell carcinoma have been reported with GILENYA in the postmarketing setting.

Skin examinations are recommended prior to or shortly after the start of treatment and periodically thereafter for all patients, particularly those with risk factors for skin cancer. Providers and patients are advised to monitor for suspicious skin lesions. If a suspicious skin lesion is observed, it should be promptly evaluated. As usual for patients with increased risk for skin cancer, exposure to sunlight and ultraviolet light should be limited by wearing protective clothing and using a sunscreen with a high protection factor. Concomitant phototherapy with UV-B radiation or PUVA photochemotherapy is not recommended in patients taking GILENYA.

Lymphoma

Cases of lymphoma, including both T-cell and B-cell types and CNS lymphoma, have occurred in patients receiving GILENYA. The reporting rate of non-Hodgkin lymphoma with GILENYA is greater than that expected in the general population adjusted by age, gender, and region. Cutaneous T-cell lymphoma (including mycosis fungoides) has also been reported with GILENYA in the postmarketing setting.

5.13 Immune System Effects Following GILENYA Discontinuation

Fingolimod remains in the blood and has pharmacodynamic effects, including decreased lymphocyte counts, for up to 2 months following the last dose of GILENYA. Lymphocyte counts generally return to the normal range within 1 to 2 months of stopping therapy [see Clinical Pharmacology (12.2)]. Because of the continuing pharmacodynamic effects of fingolimod, initiating other drugs during this period warrants the same considerations needed for concomitant administration (e.g., risk of additive immunosuppressant effects) [see Drug Interactions (7.4)].

5.14 Hypersensitivity Reactions

Hypersensitivity reactions, including rash, urticaria, and angioedema have been reported with GILENYA in the postmarketing setting. GILENYA is contraindicated in patients with history of hypersensitivity to fingolimod or any of its excipients [see Contraindications (4)].

6 ADVERSE REACTIONS

The following serious adverse reactions are described elsewhere in labeling:

- Bradyarrhythmia and Atrioventricular Blocks [see Warnings and Precautions (5.1)]
- Infections [see Warnings and Precautions (5.2)]
- Progressive Multifocal Leukoencephalopathy [see Warnings and Precautions (5.3)]
- Macular Edema [see Warnings and Precautions (5.4)]
- Liver Injury [see Warnings and Precautions (5.5)]
- Posterior Reversible Encephalopathy Syndrome [see Warnings and Precautions (5.6)]
- Respiratory Effects [see Warnings and Precautions (5.7)]
- Fetal Risk [see Warnings and Precautions (5.8)]
- Severe Increase in Disability After Stopping GILENYA [see Warnings and Precautions (5.9)]
- Tumefactive Multiple Sclerosis [see Warnings and Precautions (5.10)]
- Increased Blood Pressure [see Warnings and Precautions (5.11)]
- Malignancies [see Warnings and Precautions (5.12)]
- Immune System Effects Following GILENYA Discontinuation [see Warnings and Precautions (5.13)]
- Hypersensitivity Reactions [see Warnings and Precautions (5.14)]

6.1 Clinical Trials Experience

Because clinical trials are conducted under widely varying conditions, adverse reaction rates observed in the clinical trials of a drug cannot be directly compared to rates in the clinical trials of another drug and may not reflect the rates observed in practice.

Adults

In clinical trials (Studies 1, 2, and 3), a total of 1212 patients with relapsing forms of multiple sclerosis received GILENYA 0.5 mg. This included 783 patients who received GILENYA 0.5 mg in the 2-year placebo-controlled trials (Studies 1 and 3) and 429 patients who received GILENYA 0.5 mg in the 1-year active-controlled trial (Study 2). The overall exposure in the controlled trials was equivalent to 1716 person-years. Approximately 1000 patients received at least 2 years of treatment with GILENYA 0.5 mg. In all clinical studies, including uncontrolled extension studies, the exposure to GILENYA 0.5 mg was approximately 4119 person-years.

In placebo-controlled trials, the most frequent adverse reactions (incidence ≥ 10% and greater than placebo) for GILENYA 0.5 mg were headache, liver transaminase elevation, diarrhea, cough, influenza, sinusitis, back pain, abdominal pain, and pain in extremity. Adverse events that led to treatment discontinuation and occurred in more than 1% of patients taking GILENYA 0.5 mg, were serum transaminase elevations (4.7% compared to 1% on placebo) and basal cell carcinoma (1% compared to 0.5% on placebo).

Table 1 lists adverse reactions in clinical studies in adults that occurred in ≥ 1% of GILENYA-treated patients and ≥ 1% higher rate than for placebo.

Table 1: Adverse Reactions Reported in Adult Studies 1 and 3 (Occurring in ≥ 1% of Patients and Reported for GILENYA 0.5 mg at ≥ 1% Higher Rate Than for Placebo)
Adverse drug reactions | GILENYA 0.5 mg N = 783 % | Placebo N = 773 %
Infections
Influenza | 11 | 8
Sinusitis | 11 | 8
Bronchitis | 8 | 5
Herpes zoster | 2 | 1
Tinea versicolor | 2 | < 1
Cardiac disorders
Bradycardia | 3 | 1
Nervous system disorders
Headache | 25 | 24
Migraine | 6 | 4
Gastrointestinal disorders
Nausea | 13 | 12
Diarrhea | 13 | 10
Abdominal pain | 11 | 10
General disorders and administration-site conditions
Asthenia | 2 | 1
Musculoskeletal and connective tissue disorders
Back pain | 10 | 9
Pain in extremity | 10 | 7
Skin and subcutaneous tissue disorders
Alopecia | 3 | 2
Actinic keratosis | 2 | 1
Investigations
Liver transaminase elevations (ALT/GGT/AST) | 15 | 4
Blood triglycerides increased | 3 | 1
Respiratory, thoracic, and mediastinal disorders
Cough | 12 | 11
Dyspnea | 9 | 7
Eye disorders
Vision blurred | 4 | 2
Vascular disorders
Hypertension | 8 | 4
Blood and lymphatic system disorders
Lymphopenia | 7 | < 1
Leukopenia | 2 | < 1
Neoplasms benign, malignant, and unspecified (including cysts and polyps)
Skin papilloma | 3 | 2
Basal cell carcinoma | 2 | 1
Abbreviations: ALT, alanine transaminase; AST, aspartate transferase; GGT, gamma-glutamyl transferase.

Adverse reactions of seizure, dizziness, pneumonia, eczema, and pruritus were also reported in Studies 1 and 3, but did not meet the reporting rate criteria for inclusion in Table 1 (difference was less than 1%).

Adverse reactions with GILENYA 0.5 mg in Study 2, the 1-year active-controlled (versus interferon beta-1a) study were generally similar to those in Studies 1 and 3.

Vascular Events

Vascular events, including ischemic and hemorrhagic strokes, and peripheral arterial occlusive disease were reported in premarketing clinical trials in patients who received GILENYA doses (1.25 mg to 5 mg) higher than recommended for use in MS. Similar events have been reported with GILENYA in the postmarketing setting although a causal relationship has not been established.

Seizure

Cases of seizures, including status epilepticus, have been reported with the use of GILENYA in clinical trials and in the postmarketing setting in adults [see Adverse Reactions (6.2)]. In adult clinical trials, the rate of seizures was 0.9% in GILENYA-treated patients and 0.3% in placebo-treated patients. It is unknown whether these events were related to the effects of multiple sclerosis alone, to GILENYA, or to a combination of both.

Pediatric Patients 10 Years of Age and Older

In the controlled pediatric trial (Study 4), the safety profile in pediatric patients receiving GILENYA 0.25 mg or 0.5 mg daily was similar to that seen in adult patients.

In the pediatric study, cases of seizures were reported in 5.6% of GILENYA-treated patients and 0.9% of interferon beta-1a-treated patients [see Use in Specific Populations (8.4)].

6.2 Postmarketing Experience

The following adverse reactions have been identified during postapproval use of GILENYA. Because these reactions are reported voluntarily from a population of uncertain size, it is not always possible to reliably estimate their frequency or establish a causal relationship to drug exposure.

Blood and Lymphatic System Disorders: Hemolytic anemia and thrombocytopenia

Hepatobiliary Disorders: Liver injury [see Warnings and Precautions (5.5)]

Infections: Infections, including cryptococcal infections [see Warnings and Precautions (5.2)], human papilloma virus (HPV) infection, including papilloma, dysplasia, warts and HPV-related cancer [see Warnings and Precautions (5.2)], progressive multifocal leukoencephalopathy [see Warnings and Precautions (5.3)]

Musculoskeletal and Connective Tissue Disorders: Arthralgia, myalgia

Nervous System Disorders: Posterior reversible encephalopathy syndrome [see Warnings and Precautions (5.6)], seizures, including status epilepticus [see Adverse Reactions (6.1)]

Neoplasms, Benign, Malignant, and Unspecified (including cysts and polyps): Melanoma, Merkel cell carcinoma, cutaneous T-cell lymphoma (including mycosis fungoides), Kaposi’s sarcoma, squamous cell carcinoma [see Warnings and Precautions (5.12)]

Skin and Subcutaneous Tissue Disorders: Hypersensitivity [see Warnings and Precautions (5.14)]

7 DRUG INTERACTIONS

7.1 QT Prolonging Drugs

GILENYA has not been studied in patients treated with drugs that prolong the QT interval. Drugs that prolong the QT interval have been associated with cases of torsades de pointes in patients with bradycardia. Since initiation of GILENYA treatment results in decreased heart rate and may prolong the QT interval, patients on QT-prolonging drugs with a known risk of torsades de pointes (e.g., citalopram, chlorpromazine, haloperidol, methadone, erythromycin) should be monitored overnight with continuous ECG in a medical facility [see Dosage and Administration (2.4), Warnings and Precautions (5.1)].

7.2 Ketoconazole

The blood levels of fingolimod and fingolimod-phosphate are increased by 1.7-fold when used concomitantly with ketoconazole. Patients who use GILENYA and systemic ketoconazole concomitantly should be closely monitored, as the risk of adverse reactions is increased.

7.3 Vaccines

GILENYA reduces the immune response to vaccination. Vaccination may be less effective during and for up to 2 months after discontinuation of treatment with GILENYA [see Clinical Pharmacology (12.2)]. Avoid the use of live attenuated vaccines during and for 2 months after treatment with GILENYA because of the risk of infection. It is recommended that pediatric patients, if possible, be brought up to date with all immunizations in agreement with current immunization guidelines prior to initiating GILENYA therapy.

7.4 Antineoplastic, Immunosuppressive, or Immune-Modulating Therapies

Antineoplastic, immune-modulating, or immunosuppressive therapies, (including corticosteroids) are expected to increase the risk of immunosuppression, and the risk of additive immune system effects must be considered if these therapies are coadministered with GILENYA. When switching from drugs with prolonged immune effects, such as natalizumab, teriflunomide or mitoxantrone, the duration and mode of action of these drugs must be considered to avoid unintended additive immunosuppressive effects when initiating GILENYA [see Warnings and Precautions (5.2)].

7.5 Drugs That Slow Heart Rate or Atrioventricular Conduction (e.g., beta blockers or diltiazem)

Experience with GILENYA in patients receiving concurrent therapy with drugs that slow the heart rate or AV conduction (e.g., beta blockers, digoxin, or heart rate-slowing calcium channel blockers, such as diltiazem or verapamil) is limited. Because initiation of GILENYA treatment may result in an additional decrease in heart rate, concomitant use of these drugs during GILENYA initiation may be associated with severe bradycardia or heart block. Seek advice from the physician prescribing these drugs regarding the possibility to switch to drugs that do not slow the heart rate or atrioventricular conduction before initiating GILENYA. Patients who cannot switch should have overnight continuous ECG monitoring after the first dose [see Dosage and Administration (2.4), Warnings and Precautions (5.1)].

7.6 Laboratory Test Interaction

Because GILENYA reduces blood lymphocyte counts via redistribution in secondary lymphoid organs, peripheral blood lymphocyte counts cannot be utilized to evaluate the lymphocyte subset status of a patient treated with GILENYA. A recent CBC should be available before initiating treatment with GILENYA.

8 USE IN SPECIFIC POPULATIONS

8.1 Pregnancy

Risk Summary

Available observational pregnancy registry data suggest that use of GILENYA is associated with an increased prevalence of major birth defects in comparison to the general population. However, limitations in the number of exposed pregnant women and in the study design preclude definitive conclusions (see Data). Data from prospective reports to the pregnancy registry are currently not sufficient to allow for an adequate assessment of the drug-associated risk for miscarriage.

Based on findings from animal studies, GILENYA may cause fetal harm when administered to a pregnant woman.

In oral studies conducted in rats and rabbits, fingolimod demonstrated developmental toxicity, including an increase in malformations (rats) and embryolethality, when given to pregnant animals. In rats, the highest no-effect dose was less than the recommended human dose of 0.5 mg/day on a body surface area (mg/m^2) basis. The most common fetal visceral malformations in rats were persistent truncus arteriosus and ventricular septal defect. The receptor affected by fingolimod (sphingosine 1-phosphate receptor) is known to be involved in vascular formation during embryogenesis (see Data). Advise pregnant women of the potential risk to a fetus.

In the US general population, the estimated background risk of major birth defects and miscarriage in clinically recognized pregnancies is 2% to 4% and 15% to 20%, respectively. The background risk of major birth defects and miscarriage for the indicated population is unknown.

Clinical Considerations

In females planning to become pregnant, GILENYA should be stopped 2 months before planned conception.

The possibility of severe increase in disability should be considered in women who discontinue or are considering discontinuation of GILENYA because of pregnancy or planned pregnancy. In many of the cases in which increase in disability was reported after stopping GILENYA, patients had stopped GILENYA because of pregnancy or planned pregnancy [see Warnings and Precautions (5.9)].

Data

Human Data

In a prospective observational GILENYA pregnancy registry (GPR) (2011 - 2024), the rate of major birth defects among 147 live births, stillbirths, or terminations of pregnancy due to fetal anomalies from women who were administered fingolimod during the first trimester was 8.2% (95% CI: 4.3-13.8) using the European Registration of Congenital Anomalies and Twin classification and 10.9% (95% CI: 6.4-17.1) using the Metropolitan Atlanta Congenital Defects Program classification. The most frequent major birth defects were congenital heart defects, renal/urinary malformations, and limb/musculoskeletal malformations. Study limitations include no adjustment for confounders, no re-adjudication in case of spontaneous resolution, lack of an internal comparator cohort, and small sample size.

In fingolimod prospective pharmacovigilance data, the most frequent major birth defect types were similar to those reported in the GPR.

The pattern of malformations reported for GILENYA is similar to that observed in the general population. There is no evidence of clustering of specific birth defects with GILENYA.

Animal Data

When fingolimod was orally administered to pregnant rats during the period of organogenesis (0, 0.03, 0.1, and 0.3 mg/kg/day or 0, 1, 3, and 10 mg/kg/day), increased incidences of fetal malformations and embryofetal deaths were observed at all but the lowest dose tested (0.03 mg/kg/day), which is less than the recommended human dose (RHD) on a mg/m^2 basis. Oral administration to pregnant rabbits during organogenesis (0, 0.5, 1.5, and 5 mg/kg/day) resulted in increased incidences of embryofetal mortality and fetal growth retardation at the mid and high doses. The no-effect dose for these effects in rabbits (0.5 mg/kg/day) is approximately 20 times the RHD on a mg/m^2 basis.

When fingolimod was orally administered to female rats during pregnancy and lactation (0, 0.05, 0.15, and 0.5 mg/kg/day), pup survival was decreased at all doses and a neurobehavioral (learning) deficit was seen in offspring at the high dose. The low-effect dose of 0.05 mg/kg/day is similar to the RHD on a mg/m^2 basis.

8.2 Lactation

Risk Summary

There are no data on the presence of fingolimod in human milk, the effects on the breastfed infant, or the effects of the drug on milk production. Fingolimod is excreted in the milk of treated rats. When a drug is present in animal milk, it is likely that the drug will be present in human milk. The developmental and health benefits of breastfeeding should be considered along with the mother’s clinical need for GILENYA and any potential adverse effects on the breastfed infant from GILENYA or from the underlying maternal condition.

8.3 Females and Males of Reproductive Potential

Pregnancy Testing

The pregnancy status of females of reproductive potential should be verified prior to starting treatment with GILENYA [see Use in Specific Populations (8.1)].

Contraception

Before initiation of GILENYA treatment, females of reproductive potential should be counseled on the potential for a serious risk to the fetus and the need for effective contraception during treatment with GILENYA [see Warnings and Precautions (5.8) and Use in Specific Populations (8.1)]. Since it takes approximately 2 months to eliminate the compound from the body after stopping treatment, the potential risk to the fetus may persist and women should use effective contraception during this period [see Warnings and Precautions (5.8, 5.13)].

8.4 Pediatric Use

Safety and effectiveness of GILENYA for the treatment of relapsing forms of multiple sclerosis in pediatric patients 10 to less than 18 years of age were established in one randomized, double-blind clinical study in 215 patients (GILENYA n = 107; intramuscular interferon (IFN) beta-1a n = 108) [see Clinical Studies (14.2)].

In the controlled pediatric study, the safety profile in pediatric patients (10 to less than 18 years of age) receiving GILENYA 0.25 mg or 0.5 mg daily was similar to that seen in adult patients. In the pediatric study, cases of seizures were reported in 5.6% of GILENYA-treated patients and 0.9% of interferon beta-1a-treated patients.

It is recommended that pediatric patients, if possible, complete all immunizations in accordance with current immunization guidelines prior to initiating GILENYA therapy.

Safety and effectiveness of GILENYA in pediatric patients below the age of 10 years have not been established.

Juvenile Animal Toxicity Data

In a study in which fingolimod (0.3, 1.5, or 7.5 mg/kg/day) was orally administered to young rats from weaning through sexual maturity, changes in bone mineral density and persistent neurobehavioral impairment (altered auditory startle) were observed at all doses. Delayed sexual maturation was noted in females at the highest dose tested and in males at all doses. The bone changes observed in fingolimod-treated juvenile rats are consistent with a reported role of S1P in the regulation of bone mineral homeostasis.

When fingolimod (0.5 or 5 mg/kg/day) was orally administered to rats from the neonatal period through sexual maturity, a marked decrease in T-cell dependent antibody response was observed at both doses. This effect had not fully recovered by 6 to 8 weeks after the end of treatment.

Overall, a no-effect dose for adverse developmental effects in juvenile animals was not identified.

8.5 Geriatric Use

Clinical MS studies of GILENYA did not include sufficient numbers of patients aged 65 years and over to determine whether they respond differently than younger patients. GILENYA should be used with caution in patients aged 65 years and over, reflecting the greater frequency of decreased hepatic, or renal, function and of concomitant disease or other drug therapy.

8.6 Hepatic Impairment

Because fingolimod, but not fingolimod-phosphate, exposure is doubled in patients with severe hepatic impairment, patients with severe hepatic impairment should be closely monitored, as the risk of adverse reactions may be greater [see Warnings and Precautions (5.5), Clinical Pharmacology (12.3)].

No dose adjustment is needed in patients with mild or moderate hepatic impairment.

8.7 Renal Impairment

The blood level of some GILENYA metabolites is increased (up to 13-fold) in patients with severe renal impairment [see Clinical Pharmacology (12.3)]. The toxicity of these metabolites has not been fully explored. The blood level of these metabolites has not been assessed in patients with mild or moderate renal impairment.

10 OVERDOSAGE

GILENYA can induce bradycardia as well as AV conduction blocks (including complete AV block). The decline in heart rate usually starts within 1 hour of the first dose and is maximal within 6 hours in most patients [see Warnings and Precautions (5.1)]. In case of GILENYA overdosage, observe patients overnight with continuous ECG monitoring in a medical facility, and obtain regular measurements of blood pressure [see Dosage and Administration (2.4)].

Neither dialysis nor plasma exchange results in removal of fingolimod from the body.

11 DESCRIPTION

Fingolimod is a sphingosine 1-phosphate receptor modulator.

Chemically, fingolimod is 2-amino-2-[2-(4-octylphenyl)ethyl]propan-1,3-diol hydrochloride. Its structure is shown below:

Fingolimod hydrochloride is a white to practically white powder that is freely soluble in water and alcohol and soluble in propylene glycol. It has a molecular weight of 343.93 g/mol.

GILENYA is provided as 0.25 mg and 0.5 mg hard gelatin capsules for oral use.

Each 0.25 mg capsule contains 0.28 mg of fingolimod hydrochloride, equivalent to 0.25 mg fingolimod.

Each 0.5 mg capsule contains 0.56 mg of fingolimod hydrochloride, equivalent to 0.5 mg of fingolimod.

Each GILENYA 0.25 mg capsule contains the following inactive ingredients: gelatin, hydroxypropylbetadex, hydroxypropylcellulose, magnesium stearate, mannitol, titanium dioxide, and yellow iron oxide.

Each GILENYA 0.5 mg capsule contains the following inactive ingredients: gelatin, magnesium stearate, mannitol, titanium dioxide, and yellow iron oxide.

12 CLINICAL PHARMACOLOGY

12.1 Mechanism of Action

Fingolimod is metabolized by sphingosine kinase to the active metabolite, fingolimod-phosphate. Fingolimod-phosphate is a sphingosine 1-phosphate receptor modulator, and binds with high affinity to sphingosine 1-phosphate receptors 1, 3, 4, and 5. Fingolimod-phosphate blocks the capacity of lymphocytes to egress from lymph nodes, reducing the number of lymphocytes in peripheral blood. The mechanism by which fingolimod exerts therapeutic effects in multiple sclerosis is unknown, but may involve reduction of lymphocyte migration into the central nervous system.

12.2 Pharmacodynamics

Heart Rate and Rhythm

Fingolimod causes a transient reduction in heart rate and AV conduction at treatment initiation [see Warnings and Precautions (5.1)].

Heart rate progressively increases after the first day, returning to baseline values within 1 month of the start of chronic treatment.

Autonomic responses of the heart, including diurnal variation of heart rate and response to exercise, are not affected by fingolimod treatment.

Fingolimod treatment is not associated with a decrease in cardiac output.

Potential to Prolong the QT Interval

In a thorough QT interval study of doses of 1.25 or 2.5 mg fingolimod at steady-state, when a negative chronotropic effect of fingolimod was still present, fingolimod treatment resulted in a prolongation of QTc, with the upper boundary of the 90% confidence interval (CI) of 14.0 msec. There is no consistent signal of increased incidence of QTc outliers, either absolute or change from baseline, associated with fingolimod treatment. In MS studies, there was no clinically relevant prolongation of the QT interval, but patients at risk for QT prolongation were not included in clinical studies.

Immune System

Effects on Immune Cell Numbers in the Blood

In a study in which 12 adult subjects received GILENYA 0.5 mg daily, the lymphocyte count decreased to approximately 60% of baseline within 4 to 6 hours after the first dose. With continued daily dosing, the lymphocyte count continued to decrease over a 2-week period, reaching a nadir count of approximately 500 cells/mcL or approximately 30% of baseline. In a placebo-controlled study in 1272 MS patients (of whom 425 received fingolimod 0.5 mg daily and 418 received placebo), 18% (N = 78) of patients on fingolimod 0.5 mg reached a nadir of < 200 cells/mcL on at least 1 occasion. No patient on placebo reached a nadir of < 200 cells/mcL. Low lymphocyte counts are maintained with chronic daily dosing of GILENYA 0.5 mg daily.

Chronic fingolimod dosing leads to a mild decrease in the neutrophil count to approximately 80% of baseline. Monocytes are unaffected by fingolimod.

Peripheral lymphocyte count increases are evident within days of stopping fingolimod treatment and typically normal counts are reached within 1 to 2 months.

Effect on Antibody Response

GILENYA reduces the immune response to vaccination, as evaluated in 2 studies.

In the first study, the immunogenicity of keyhole limpet hemocyanin (KLH) and pneumococcal polysaccharide vaccine (PPV-23) immunization were assessed by IgM and IgG titers in a steady-state, randomized, placebo-controlled study in healthy adult volunteers. Compared to placebo, antigen-specific IgM titers were decreased by 91% and 25% in response to KLH and PPV-23, respectively, in subjects on GILENYA 0.5 mg. Similarly, IgG titers were decreased by 45% and 50%, in response to KLH and PPV-23, respectively, in subjects on GILENYA 0.5 mg daily compared to placebo. The responder rate for GILENYA 0.5 mg as measured by the number of subjects with a > 4-fold increase in KLH IgG was comparable to placebo and 25% lower for PPV-23 IgG, while the number of subjects with a > 4-fold increase in KLH and PPV-23 IgM was 75% and 40% lower, respectively, compared to placebo. The capacity to mount a skin delayed-type hypersensitivity reaction to Candida and tetanus toxoid was decreased by approximately 30% in subjects on GILENYA 0.5 mg daily, compared to placebo. Immunologic responses were further decreased with fingolimod 1.25 mg (a dose higher than recommended in MS) [see Warnings and Precautions (5.2)].

In the second study, the immunogenicity of Northern hemisphere seasonal influenza and tetanus toxoid vaccination was assessed in a 12-week steady-state, randomized, placebo-controlled study of GILENYA 0.5 mg in adult multiple sclerosis patients (n = 136). The responder rate 3 weeks after vaccination, defined as seroconversion or a ≥ 4-fold increase in antibody directed against at least 1 of the 3 influenza strains, was 54% for GILENYA 0.5 mg and 85% in the placebo group. The responder rate 3 weeks after vaccination, defined as seroconversion or a ≥ 4-fold increase in antibody directed against tetanus toxoid was 40% for GILENYA 0.5 mg and 61% in the placebo group.

Pulmonary Function

Single fingolimod doses ≥ 5 mg (10-fold the recommended dose) are associated with a dose-dependent increase in airway resistance. In a 14-day study of 0.5, 1.25, or 5 mg/day, fingolimod was not associated with impaired oxygenation or oxygen desaturation with exercise or an increase in airway responsiveness to methacholine. Subjects on fingolimod treatment had a normal bronchodilator response to inhaled beta-agonists.

In a 14-day placebo-controlled study of adult patients with moderate asthma, no effect was seen for GILENYA 0.5 mg (recommended dose in MS). A 10% reduction in mean FEV1 at 6 hours after dosing was observed in adult patients receiving fingolimod 1.25 mg (a dose higher than recommended for use in MS) on Day 10 of treatment. Fingolimod 1.25 mg was associated with a 5-fold increase in the use of rescue short-acting beta-agonists.

12.3 Pharmacokinetics

Absorption

The Tmax of fingolimod is 12 to 16 hours. The apparent absolute oral bioavailability is 93%.

Food intake does not alter Cmax or (AUC) of fingolimod or fingolimod-phosphate. Therefore, GILENYA may be taken without regard to meals.

Steady-state blood concentrations are reached within 1 to 2 months following once-daily administration and steady-state levels are approximately 10-fold greater than with the initial dose.

Distribution

Fingolimod highly (86%) distributes in red blood cells. Fingolimod-phosphate has a smaller uptake in blood cells of < 17%. Fingolimod and fingolimod-phosphate are > 99.7% protein bound. Fingolimod and fingolimod-phosphate protein binding is not altered by renal or hepatic impairment.

Fingolimod is extensively distributed to body tissues with a volume of distribution of about 1200 ± 260 L.

Metabolism

The biotransformation of fingolimod in humans occurs by 3 main pathways: by reversible stereoselective phosphorylation to the pharmacologically active (S)-enantiomer of fingolimod-phosphate, by oxidative biotransformation catalyzed mainly by the cytochrome P450 4F2 (CYP4F2) and possibly other CYP4F isoenzymes with subsequent fatty acid-like degradation to inactive metabolites, and by formation of pharmacologically inactive non-polar ceramide analogs of fingolimod.

Inhibitors or inducers of CYP4F2 and possibly other CYP4F isozymes might alter the exposure of fingolimod or fingolimod-phosphate. In vitro studies in hepatocytes indicated that CYP3A4 may contribute to fingolimod metabolism in the case of strong induction of CYP3A4.

Following single oral administration of [^14C] fingolimod, the major fingolimod-related components in blood, as judged from their contribution to the AUC up to 816 hours post-dose of total radiolabeled components, are fingolimod itself (23.3%), fingolimod-phosphate (10.3%), and inactive metabolites [M3 carboxylic acid metabolite (8.3%), M29 ceramide metabolite (8.9%), and M30 ceramide metabolite (7.3%)].

Elimination

Fingolimod blood clearance is 6.3 ± 2.3 L/h, and the average apparent terminal half-life (t1/2) is 6 to 9 days. Blood levels of fingolimod-phosphate decline in parallel with those of fingolimod in the terminal phase, yielding similar half-lives for both.

After oral administration, about 81% of the dose is slowly excreted in the urine as inactive metabolites. Fingolimod and fingolimod-phosphate are not excreted intact in urine but are the major components in the feces with amounts of each representing less than 2.5% of the dose.

Specific Populations

Pediatric Patients

The median fingolimod-phosphate (fingolimod-P) concentration in pediatric MS patients aged 10 to less than 18 years was 1.10 ng/mL, as compared to 1.35 ng/mL in adult MS patients.

Geriatric Patients

The mechanism for elimination and results from population pharmacokinetics suggest that dose adjustment would not be necessary in elderly patients. However, clinical experience in patients aged above 65 years is limited.

Gender

Gender has no clinically significant influence on fingolimod and fingolimod-phosphate pharmacokinetics.

Race

The effects of race on fingolimod and fingolimod-phosphate pharmacokinetics cannot be adequately assessed due to a low number of patients who self-identified as Black or African American, Asian, or other races in the clinical program.

Renal Impairment

In adult patients with severe renal impairment, fingolimod Cmax and AUC are increased by 32% and 43%, respectively, and fingolimod-phosphate Cmax and AUC are increased by 25% and 14%, respectively, with no change in apparent elimination half-life. Based on these findings, the GILENYA 0.5 mg dose is appropriate for use in adult patients with renal impairment. GILENYA 0.25 mg and 0.5 mg are appropriate for use in pediatric patients with renal impairment. The systemic exposure of 2 metabolites (M2 and M3) is increased by 3- and 13-fold, respectively. The toxicity of these metabolites has not been fully characterized.

A study in patients with mild or moderate renal impairment has not been conducted.

Hepatic Impairment

In subjects with mild, moderate, or severe hepatic impairment (Child-Pugh class A, B, and C), no change in fingolimod Cmax was observed, but fingolimod AUC0-∞ was increased respectively by 12%, 44%, and 103%. In patients with severe hepatic impairment (Child-Pugh class C), fingolimod-phosphate Cmax was decreased by 22% and AUC0-96 hours was decreased by 29%. The pharmacokinetics of fingolimod-phosphate was not evaluated in patients with mild or moderate hepatic impairment. The apparent elimination half-life of fingolimod is unchanged in subjects with mild hepatic impairment, but is prolonged by about 50% in patients with moderate or severe hepatic impairment.

Patients with severe hepatic impairment (Child-Pugh class C) should be closely monitored, as the risk of adverse reactions is greater [see Warnings and Precautions (5.5)].

No dose adjustment is needed in patients with mild or moderate hepatic impairment (Child-Pugh class A and B).

Drug Interactions

Ketoconazole

The coadministration of ketoconazole (a potent inhibitor of CYP3A and CYP4F) 200 mg twice-daily at steady-state and a single dose of fingolimod 5 mg led to a 70% increase in AUC of fingolimod and fingolimod-phosphate. Patients who use GILENYA and systemic ketoconazole concomitantly should be closely monitored, as the risk of adverse reactions is greater [see Drug Interactions (7.2)].

Carbamazepine

The coadministration of carbamazepine (a potent CYP450 enzyme inducer) 600 mg twice-daily at steady-state and a single dose of fingolimod 2 mg decreased blood concentrations (AUC) of fingolimod and fingolimod-phosphate by approximately 40%. The clinical impact of this decrease is unknown.

Other strong CYP450 enzyme inducers, e.g., rifampicin, phenytoin, phenobarbital, and St. John’s wort, may also reduce AUC of fingolimod and fingolimod-phosphate. The clinical impact of this potential decrease is unknown.

Potential of Fingolimod and Fingolimod-phosphate to Inhibit the Metabolism of Comedications

In vitro inhibition studies using pooled human liver microsomes and specific metabolic probe substrates demonstrate that fingolimod has little or no capacity to inhibit the activity of the following CYP enzymes: CYP1A2, CYP2A6, CYP2B6, CYP2C8, CYP2C9, CYP2C19, CYP2D6, CYP2E1, CYP3A4/5, or CYP4A9/11 (fingolimod only), and similarly fingolimod-phosphate has little or no capacity to inhibit the activity of CYP1A2, CYP2A6, CYP2B6, CYP2C8, CYP2C9, CYP2C19, CYP2D6, CYP2E1, or CYP3A4 at concentrations up to 3 orders of magnitude of therapeutic concentrations. Therefore, fingolimod and fingolimod-phosphate are unlikely to reduce the clearance of drugs that are mainly cleared through metabolism by the major CYP isoenzymes described above.

Potential of Fingolimod and Fingolimod-phosphate to Induce its Own and/or the Metabolism of Comedications

Fingolimod was examined for its potential to induce human CYP3A4, CYP1A2, CYP4F2, and MDR1 (P-glycoprotein) mRNA and CYP3A, CYP1A2, CYP2B6, CYP2C8, CYP2C9, CYP2C19, and CYP4F2 activity in primary human hepatocytes. Fingolimod did not induce mRNA or activity of the different CYP enzymes and MDR1 with respect to the vehicle control; therefore, no clinically relevant induction of the tested CYP enzymes or MDR1 by fingolimod are expected at therapeutic concentrations. Fingolimod-phosphate was also examined for its potential to induce mRNA and/or activity of human CYP1A2, CYP2B6, CYP2C8, CYP2C9, CYP2C19, CYP3A, CYP4F2, CYP4F3B, and CYP4F12. Fingolimod-phosphate is not expected to have clinically significant induction effects on these enzymes at therapeutic doses of fingolimod. In vitro experiments did not provide an indication of CYP induction by fingolimod-phosphate.

Transporters

Based on in vitro data, fingolimod as well as fingolimod-phosphate are not expected to inhibit the uptake of comedications and/or biologics transported by the organic anion transporting polypeptides OATP1B1, OATP1B3, or the sodium taurocholate co-transporting polypeptide (NTCP). Similarly, they are not expected to inhibit the efflux of comedications and/or biologics transported by the breast cancer resistance protein (BCRP), the bile salt export pump (BSEP), the multidrug resistance-associated protein 2 (MRP2), or P-glycoprotein (P-gp) at therapeutic concentrations.

Oral Contraceptives

The coadministration of fingolimod 0.5 mg daily with oral contraceptives (ethinylestradiol and levonorgestrel) did not elicit any clinically significant change in oral contraceptives exposure. Fingolimod and fingolimod-phosphate exposure were consistent with those from previous studies. No interaction studies have been performed with oral contraceptives containing other progestagens; however, an effect of fingolimod on their exposure is not expected.

Cyclosporine

The pharmacokinetics of single-dose fingolimod was not altered during coadministration with cyclosporine at steady-state, nor was cyclosporine steady-state pharmacokinetics altered by fingolimod. These data indicate that GILENYA is unlikely to reduce or increase the clearance of drugs cleared mainly by CYP3A4. Potent inhibition of transporters MDR1 (P-gp), MRP2, and OATP-1B1 does not influence fingolimod disposition.

Isoproterenol, Atropine, Atenolol, and Diltiazem

Single-dose fingolimod and fingolimod-phosphate exposure was not altered by coadministered isoproterenol or atropine. Likewise, the single-dose pharmacokinetics of fingolimod and fingolimod-phosphate and the steady-state pharmacokinetics of both atenolol and diltiazem were unchanged during the coadministration of the latter 2 drugs individually with fingolimod.

Population Pharmacokinetics Analysis

A population pharmacokinetics evaluation performed in MS patients did not provide evidence for a significant effect of fluoxetine and paroxetine (strong CYP2D6 inhibitors) on fingolimod or fingolimod-phosphate predose concentrations. In addition, the following commonly coprescribed substances had no clinically relevant effect (< 20%) on fingolimod or fingolimod-phosphate predose concentrations: baclofen, gabapentin, oxybutynin, amantadine, modafinil, amitriptyline, pregabalin, and corticosteroids.

13 NONCLINICAL TOXICOLOGY

13.1 Carcinogenesis, Mutagenesis, Impairment of Fertility

Oral carcinogenicity studies of fingolimod were conducted in mice and rats. In mice, fingolimod was administered at oral doses of 0, 0.025, 0.25, and 2.5 mg/kg/day for up to 2 years. The incidence of malignant lymphoma was increased in males and females at the mid and high dose. The lowest dose tested (0.025 mg/kg/day) is less than the RHD of 0.5 mg/day on a body surface area (mg/m^2) basis. In rats, fingolimod was administered at oral doses of 0, 0.05, 0.15, 0.5, and 2.5 mg/kg/day. No increase in tumors was observed. The highest dose tested (2.5 mg/kg/day) is approximately 50 times the RHD on a mg/m^2 basis.

Fingolimod was negative in a battery of in vitro (Ames, mouse lymphoma thymidine kinase, chromosomal aberration in mammalian cells) and in vivo (micronucleus in mouse and rat) assays.

When fingolimod was administered orally (0, 1, 3, and 10 mg/kg/day) to male and female rats prior to and during mating, and continuing to Day 7 of gestation in females, no effect on fertility was observed up to the highest dose tested (10 mg/kg), which is approximately 200 times the RHD on a mg/m^2 basis.

13.2 Animal Toxicology and/or Pharmacology

Lung toxicity was observed in 2 different strains of rats and in dogs and monkeys. The primary findings included increase in lung weight, associated with smooth muscle hypertrophy, hyperdistention of the alveoli, and/or increased collagen. Insufficient or lack of pulmonary collapse at necropsy, generally correlated with microscopic changes, was observed in all species. In rats and monkeys, lung toxicity was observed at all oral doses tested in chronic studies. The lowest doses tested in rats (0.05 mg/kg/day in the 2-year carcinogenicity study) and monkeys (0.5 mg/kg/day in the 39-week toxicity study) are similar to and approximately 20 times the RHD on a mg/m^2 basis, respectively.

In the 52-week oral study in monkeys, respiratory distress associated with ketamine administration was observed at doses of 3 and 10 mg/kg/day; the most affected animal became hypoxic and required oxygenation. As ketamine is not generally associated with respiratory depression, this effect was attributed to fingolimod. In a subsequent study in rats, ketamine was shown to potentiate the bronchoconstrictive effects of fingolimod. The relevance of these findings to humans is unknown.

14 CLINICAL STUDIES

14.1 Adults

The efficacy of GILENYA was demonstrated in 2 studies that evaluated once-daily doses of GILENYA 0.5 mg and 1.25 mg in patients with relapsing-remitting MS (RRMS). Both studies included patients who had experienced at least 2 clinical relapses during the 2 years prior to randomization or at least 1 clinical relapse during the 1 year prior to randomization, and had an Expanded Disability Status Scale (EDSS) score from 0 to 5.5. Study 1 was a 2-year randomized, double-blind, placebo-controlled study in patients with RRMS who had not received any interferon-beta or glatiramer acetate for at least the previous 3 months and had not received any natalizumab for at least the previous 6 months. Neurological evaluations were performed at screening, every 3 months and at time of suspected relapse. MRI evaluations were performed at screening, Month 6, Month 12, and Month 24. The primary endpoint was the annualized relapse rate.

Median age was 37 years, median disease duration was 6.7 years and median EDSS score at baseline was 2.0. Patients were randomized to receive GILENYA 0.5 mg (N = 425), 1.25 mg (N = 429), or placebo (N = 418) for up to 24 months. Median time on study drug was 717 days on 0.5 mg, 715 days on 1.25 mg, and 719 days on placebo.

The annualized relapse rate was significantly lower in patients treated with GILENYA than in patients who received placebo. The secondary endpoint was the time to 3-month confirmed disability progression as measured by at least a 1-point increase from baseline in EDSS (0.5-point increase for patients with baseline EDSS of 5.5) sustained for 3 months. Time to onset of 3-month confirmed disability progression was significantly delayed with GILENYA treatment compared to placebo. The 1.25 mg dose resulted in no additional benefit over the GILENYA 0.5 mg dose. The results for this study are shown in Table 2 and Figure 1.

Table 2: Clinical and MRI Results of Study 1
 | GILENYA 0.5 mg N = 425 | Placebo N = 418 | p-value
Clinical endpoints
Annualized relapse rate (primary endpoint) | 0.18 | 0.40 | < 0.001
Percentage of patients without relapse | 70% | 46% | < 0.001
Hazard ratio‡ of disability progression (95% CI) | 0.70 (0.52, 0.96) |  | 0.02
MRI endpoint
Mean (median) number of new or newly enlarging T2 lesions over 24 months | 2.5 (0) | 9.8 (5.0) | < 0.001
Mean (median) number of T1 Gd-enhancing lesions at Month 24 | 0.2 (0) | 1.1 (0) | < 0.001
Abbreviation: CI, confidence interval.
All analyses of clinical endpoints were intent-to-treat. MRI analysis used evaluable dataset.
‡Hazard ratio is an estimate of the relative risk of having the event of disability progression on GILENYA as compared to placebo.

Figure 1: Time to 3-Month Confirmed Disability Progression – Study 1 (ITT population)

Study 2 was a 1-year randomized, double-blind, double-dummy, active-controlled study in patients with RRMS who had not received any natalizumab in the previous 6 months. Prior therapy with interferon-beta or glatiramer acetate up to the time of randomization was permitted.

Neurological evaluations were performed at screening, every 3 months, and at the time of suspected relapses. MRI evaluations were performed at screening and at Month 12. The primary endpoint was the annualized relapse rate.

Median age was 36 years, median disease duration was 5.9 years, and median EDSS score at baseline was 2.0. Patients were randomized to receive GILENYA 0.5 mg (N = 431), 1.25 mg (N = 426), or interferon beta-1a, 30 mcg via the intramuscular route (IM) once-weekly (N = 435) for up to 12 months. Median time on study drug was 365 days on GILENYA 0.5 mg, 354 days on 1.25 mg, and 361 days on interferon beta-1a IM.

The annualized relapse rate was significantly lower in patients treated with GILENYA 0.5 mg than in patients who received interferon beta-1a IM. The key secondary endpoints were number of new and newly enlarging T2 lesions and time to onset of 3-month confirmed disability progression as measured by at least a 1-point increase from baseline in EDSS (0.5-point increase for those with baseline EDSS of 5.5) sustained for 3 months. The number of new and newly enlarging T2 lesions was significantly lower in patients treated with GILENYA than in patients who received interferon beta-1a IM. There was no significant difference in the time to 3-month confirmed disability progression between GILENYA and interferon beta-1a-treated patients at 1 year. The 1.25 mg dose resulted in no additional benefit over the GILENYA 0.5 mg dose. The results for this study are shown in Table 3.

Table 3: Clinical and MRI Results of Study 2
 | GILENYA 0.5 mg N = 429 | Interferon beta-1a IM 30 mcg N = 431 | p-value
Clinical endpoints
Annualized relapse rate (primary endpoint) | 0.16 | 0.33 | < 0.001
Percentage of patients without relapse | 83% | 70% | < 0.001
Hazard ratio‡ of disability progression (95% CI) | 0.71 (0.42, 1.21) |  | 0.21
MRI endpoint
Mean (median) number of new or newly enlarging T2 lesions over 12 months | 1.6 (0) | 2.6 (1.0) | 0.002
Mean (median) number of T1 Gd-enhancing lesions at Month 12 | 0.2 (0) | 0.5 (0) | < 0.001
Abbreviation: CI, confidence interval.
All analyses of clinical endpoints were intent-to-treat. MRI analysis used evaluable dataset.
‡Hazard ratio is an estimate of the relative risk of having the event of disability progression on GILENYA as compared to control.

Pooled results of Study 1 and Study 2 showed a consistent and statistically significant reduction of annualized relapse rate compared to comparator in subgroups defined by gender, age, prior MS therapy, and disease activity.

14.2 Pediatric Patients (10 to less than 18 Years of Age)

Study 4 (NCT 01892722) evaluated the efficacy of once-daily oral doses of GILENYA 0.25 mg or GILENYA 0.5 mg in pediatric patients 10 to less than 18 years of age with relapsing-remitting multiple sclerosis. Study 4 was a 215-patient, double-blind, randomized, clinical trial that compared GILENYA to intramuscular interferon beta-1a. Prior therapy with interferon-beta, dimethyl fumarate, or glatiramer acetate up to the time of randomization was permitted. The study included patients who had experienced at least 1 clinical relapse during the year prior or 2 relapses during the 2 years prior to screening, or evidence of 1 or more Gd-enhancing lesions on MRI within 6 months prior to randomization, and had an EDSS score from 0 to 5.5. Neurological evaluations were scheduled at screening, every 3 months, and at the time of suspected relapses. MRI evaluations were performed at screening and every 6 months throughout the study. The primary endpoint was the annualized relapse rate.

At baseline, the median age was 16 years, median disease duration since first symptom was 1.5 years, and median EDSS score was 1.5. One patient received no study drug and is excluded from the analysis of efficacy. Median duration of exposure to study drug was 634 days in the GILENYA group (n = 107) and 547 days in the interferon beta-1a group (n = 107). In the GILENYA group, 6.5% of patients did not complete the study, compared to 18.5% in the interferon beta-1a group.

The primary endpoint, the annualized relapse rate (ARR), was significantly lower in patients treated with GILENYA (0.122) than in patients who received interferon beta-1a (0.675). Relative reduction in ARR was 81.9%. The annualized rate of the number of new or newly enlarged T2 lesions up to Month 24 (key secondary endpoint) was significantly lower in patients treated with GILENYA, as was the number of Gd-enhancing T1 lesions per scan up to Month 24.

Table 4 summarizes the results of Study 4.

Table 4: Clinical and MRI Results of Study 4
 | GILENYA 0.25 mg or 0.5 mg PO N = 107 | Interferon beta-1a 30 mcg IM N = 107 | p-value | Relative reduction
Clinical endpoints
Annualized relapse rate (primary endpoint) | 0.122 | 0.675 | < 0.001* | 81.9%
Percent of patients remaining relapse-free at 24 months | 86.0% | 45.8%
MRI endpoints
Annualized rate of the number of new or newly enlarging T2 lesions | 4.393 | 9.269 | < 0.001* | 52.6%
Mean number of Gd-enhancing T1 lesions per scan up to Month 24 | 0.436 | 1.282 | < 0.001* | 66.0%
Abbreviations: IM, intramuscular; MRI, magnetic resonance imaging; PO, by mouth.
All analyses of clinical endpoints were on full analysis set. MRI analyses used the evaluable dataset.
*Indicates statistical significance vs. Interferon beta-1a IM at two-sided 0.05 level.

16 HOW SUPPLIED/STORAGE AND HANDLING

16.1 How Supplied

0.25 mg GILENYA capsules are supplied as follows:

hard gelatin capsules with an ivory opaque body and cap, with black radial imprint “FTY 0.25 mg” on the cap and a black radial band on the capsule body

Carton of 7 capsules containing 1 blister card of 7 capsules per blister card NDC 0078-0965-89

0.5 mg GILENYA capsules are supplied as follows:

hard gelatin capsules with a white opaque body and bright yellow cap imprinted with “FTY 0.5 mg” on the cap and 2 radial bands imprinted on the capsule body with yellow ink.

Bottle of 30 capsules NDC 0078-0607-15

16.2 Storage and Handling

GILENYA capsules should be stored at 20ºC to 25ºC (68ºF to 77ºF); excursions permitted to 15ºC to 30ºC (59ºF to 86ºF). Protect from moisture.

17 PATIENT COUNSELING INFORMATION

Advise the patient to read the FDA-approved patient labeling (Medication Guide).

Tell patients not to discontinue GILENYA without first discussing this with the prescribing healthcare provider. Advise patients to contact their healthcare provider if they accidently take more GILENYA than prescribed.

Cardiac Effects

Advise patients that initiation of GILENYA treatment results in a transient decrease in heart rate. Inform patients that they will need to be observed in the healthcare provider’s office or other facility for at least 6 hours after the first dose, after reinitiation if treatment is interrupted or discontinued for certain periods, and after the dosage is increased [see Dosage and Administration (2.4), Warnings and Precautions (5.1)].

Risk of Infections

Inform patients that they may have an increased risk of infections, some of which could be life-threatening, when taking GILENYA, and that they should contact their healthcare provider if they develop symptoms of infection. Advise patients that the use of some vaccines should be avoided during treatment with GILENYA and for 2 months after discontinuation. Recommend to patients that they delay treatment with GILENYA until after VZV vaccination if they have not had chickenpox or a previous VZV vaccination. Inform patients that prior or concomitant use of drugs that suppress the immune system may increase the risk of infection [see Warnings and Precautions (5.2)].

Progressive Multifocal Leukoencephalopathy

Inform patients that cases of progressive multifocal leukoencephalopathy (PML) have occurred in patients who received GILENYA. Inform the patient that PML is characterized by a progression of deficits and usually leads to death or severe disability over weeks or months. Instruct the patient of the importance of contacting their healthcare provider if they develop any symptoms suggestive of PML. Inform the patient that typical symptoms associated with PML are diverse, progress over days to weeks, and include progressive weakness on one side of the body or clumsiness of limbs, disturbance of vision, and changes in thinking, memory, and orientation leading to confusion and personality changes [see Warnings and Precautions (5.3)].

Macular Edema

Advise patients that GILENYA may cause macular edema, and that they should obtain an eye exam near the start of treatment with GILENYA, have their eyes monitored periodically by an eye care professional while receiving therapy, and contact their healthcare provider if they experience any changes in their vision while taking GILENYA. Inform patients with diabetes mellitus or a history of uveitis that their risk of macular edema is increased [see Warnings and Precautions (5.4)].

Hepatic Effects

Inform patients that GILENYA may cause liver injury. Advise patients that they should contact their healthcare provider if they have any unexplained nausea, vomiting, abdominal pain, fatigue, anorexia, or jaundice and/or dark urine [see Warnings and Precautions (5.5)].

Posterior Reversible Encephalopathy Syndrome

Advise patients to immediately report to their healthcare provider any symptoms involving sudden onset of severe headache, altered mental status, visual disturbances, or seizure. Inform patients that delayed treatment could lead to permanent neurological sequelae [see Warnings and Precautions (5.6)].

Respiratory Effects

Advise patients that they should contact their healthcare provider if they experience new onset or worsening of dyspnea [see Warnings and Precautions (5.7)].

Fetal Risk

- Advise pregnant women and females of reproductive potential of the potential risk to a fetus. Advise females to inform their healthcare provider of a known or suspected pregnancy [see Warnings and Precautions (5.8) and Use in Specific Populations (8.1, 8.3)].
- Advise female patients of reproductive potential to use effective contraception during treatment with GILENYA and for 2 months after the final dose [see Use in Specific Populations (8.3)].

Severe Increase in Disability After Stopping GILENYA

Inform patients that severe increase in disability has been reported after discontinuation of GILENYA. Advise patients to contact their healthcare provider if they develop worsening symptoms of MS following discontinuation of GILENYA [see Warnings and Precautions (5.9)].

Malignancies

Advise patients that the risk of basal cell carcinoma and melanoma is increased with use of GILENYA and that cases of squamous cell carcinoma, Merkel cell carcinoma, and Kaposi’s sarcoma have been reported. Advise patients that any suspicious skin lesions should be promptly evaluated. Advise patients to limit exposure to sunlight and ultraviolet light by wearing protective clothing and using a sunscreen with a high protection factor. Inform patients that lymphoma has also occurred in patients receiving GILENYA [see Warnings and Precautions (5.12)].

Persistence of GILENYA Effects After Drug Discontinuation

Advise patients that GILENYA remains in the blood and continues to have effects, including decreased blood lymphocyte counts, for up to 2 months following the last dose [see Warnings and Precautions (5.13)].

Hypersensitivity Reactions

Advise patients that GILENYA may cause hypersensitivity reactions, including rash, urticaria, and angioedema. Advise patients to contact their healthcare provider if they have any symptoms associated with hypersensitivity [see Warnings and Precautions (5.14)].

Pregnancy

Instruct patients that if they are pregnant or plan to become pregnant while taking GILENYA they should inform their healthcare provider [see Use in Specific Populations (8.1)].

GILENYA is a registered trademark of Novartis, AG.

Distributed by:
Novartis Pharmaceuticals Corporation
East Hanover, New Jersey 07936

© Novartis

T2025-53

MEDICATION GUIDE

GILENYA® (je-LEN-yah)
(fingolimod)
capsules, for oral use

Read this Medication Guide before you start taking GILENYA and each time you get a refill. There may be new information. If you are the parent of a child who is being treated with GILENYA, the following information applies to your child. This information does not take the place of talking to your healthcare provider about your medical condition or your treatment.

What is the most important information I should know about GILENYA?

GILENYA may cause serious side effects, including:
1. Slow heart rate (bradycardia or bradyarrhythmia) when you start taking GILENYA. GILENYA can cause your heart rate to slow down, especially after you take your first dose. You will have a test, called an electrocardiogram (ECG), to check the electrical activity of your heart before you take your first dose of GILENYA.
All adults and children will be observed by a healthcare professional for at least 6 hours after taking their first dose of GILENYA. Children should also be observed by a healthcare professional for at least 6 hours after taking their first dose of 0.5 mg of GILENYA when switching from the 0.25 mg dose.
After you take your first dose of GILENYA, and after a child takes their first dose of 0.5 mg of GILENYA when switching from the 0.25 mg dose:

- Your pulse and blood pressure should be checked every hour.
- You should be observed by a healthcare professional to see if you have any serious side effects. If your heart rate slows down too much, you may have symptoms, such as:
  - dizziness
  - tiredness
  - feeling like your heart is beating slowly or skipping beats
  - chest pain
- If you have any of the symptoms of slow heart rate, they will usually happen during the first 6 hours after your first dose of GILENYA. Symptoms can happen up to 24 hours after you take your first GILENYA dose.
- 6 hours after you take your first dose of GILENYA you will have another ECG. If your ECG shows any heart problems or if your heart rate is still too low or continues to decrease, you will continue to be observed.
- If you have any serious side effects after your first dose of GILENYA, especially those that require treatment with other medicines, you will stay in the medical facility to be observed overnight. You will also be observed for any serious side effects for at least 6 hours after you take your second dose of GILENYA the next day.
- If you have certain types of heart problems, or if you are taking certain types of medicines that can affect your heart, you will be observed overnight after you take your first dose of GILENYA.

Your slow heart rate will usually return to normal within 1 month after you start taking GILENYA. Call your healthcare provider or go to the nearest hospital emergency room right away if you have any symptoms of a slow heart rate.

If you miss 1 or more doses of GILENYA, you may need to be observed by a healthcare professional when you take your next dose. Call your healthcare provider if you miss a dose of GILENYA. See “How should I take GILENYA?”

2. Pregnancy. Please consult your healthcare provider before getting pregnant. You should avoid becoming pregnant while taking GILENYA or in the two months after you stop taking it because of the risk of harm to the baby.

3. Infections. GILENYA can increase your risk of serious infections that can be life-threatening and cause death. You should not receive live vaccines during treatment with GILENYA and for 2 months after you stop taking GILENYA. Talk to your healthcare provider before you receive a vaccine during treatment and for 2 months after treatment with GILENYA. If you receive a live vaccine, you may get the infection the vaccine was meant to prevent. Vaccines may not work as well when given during treatment with GILENYA.
Human Papilloma Virus (HPV). Due to risk of HPV infection please consult your healthcare provider for routine pap smear.
GILENYA lowers the number of white blood cells (lymphocytes) in your blood. This will usually go back to normal within 2 months of stopping treatment. Your healthcare provider may do a blood test to check your white blood cells before you start taking GILENYA. Call your healthcare provider right away if you have any of these symptoms of an infection during treatment with GILENYA, and for 2 months after your last dose of GILENYA:

- fever
- tiredness
- body aches
- chills
- nausea

- vomiting
- headache with fever, neck stiffness, sensitivity to light,
  nausea, or confusion (these may be symptoms of meningitis, an infection of
  the lining around your brain and spine)

4. Progressive multifocal leukoencephalopathy (PML). PML is a rare brain infection that usually leads to death or severe disability. If PML happens, it usually happens in people with weakened immune systems but has happened in people who do not have weakened immune systems. Symptoms of PML get worse over days to weeks. Call your healthcare provider right away if you have any new or worsening symptoms of PML, that have lasted several days, including:

- weakness on 1 side of your body
- loss of coordination in your arms and legs
- decreased strength
- problems with balance

- changes in your vision
- changes in your thinking or memory
- confusion
- changes in your personality

5. A problem with your vision called macular edema. Macular edema can cause some of the same vision symptoms as a multiple sclerosis (MS) attack (optic neuritis). You may not notice any symptoms with macular edema. If macular edema happens, it usually starts in the first 3 to 4 months after you start taking GILENYA but can happen at any time. Your healthcare provider should test your vision around the time you start taking GILENYA, 3 to 4 months after you start taking GILENYA, periodically while you continue taking GILENYA, and any time you notice vision changes during treatment with GILENYA. Your risk of macular edema is higher if you have diabetes or have had an inflammation of your eye called uveitis.
Call your healthcare provider right away if you have any of the following symptoms:

- blurriness or shadows in the center of your vision
- a blind spot in the center of your vision

- sensitivity to light
- unusually colored (tinted) vision

What is GILENYA?
GILENYA is a prescription medicine used to treat relapsing forms of multiple sclerosis (MS), to include clinically isolated syndrome, relapsing-remitting disease, and active secondary progressive disease, in adults and children 10 years of age and older.
It is not known if GILENYA is safe and effective in children under 10 years of age.

Who should not take GILENYA?
Do not take GILENYA if you:

- have had a heart attack, unstable angina, stroke, or mini stroke (transient ischemic attack or TIA) or certain types of heart failure in the last 6 months.
- have certain types of irregular or abnormal heartbeat (arrhythmia), including patients in whom a heart finding called prolonged QT is seen on ECG before starting GILENYA.
- have a heart rhythm problem that needs treatment with certain medicines.
- are allergic to fingolimod or any of the ingredients in GILENYA. See the end of this leaflet for a complete list of ingredients in GILENYA. Symptoms of an allergic reaction may include: rash, itchy hives, or swelling of the lips, tongue or face.

Talk to your healthcare provider before taking GILENYA if you have any of these conditions, or do not know if you have any of these conditions.

What should I tell my healthcare provider before taking GILENYA?
Before you take GILENYA, tell your healthcare provider about all your medical conditions, including if you had or now have:

- an irregular or abnormal heartbeat (arrhythmia).
- a history of stroke or mini stroke.
- heart problems, including heart attack or angina.
- a history of repeated fainting (syncope).
- a fever or infection, or you are unable to fight infections due to a disease or take or have taken medicines that lower your immune system.
- recently received a vaccine or are scheduled to receive a vaccine.
- chickenpox or have received the vaccine for chickenpox. Your healthcare provider may do a blood test for chickenpox virus. You may need to get the full course of the vaccine for chickenpox and then wait 1 month before you start taking GILENYA.
- your child has completed their vaccination schedule. Your child needs to have completed their vaccination schedule before starting treatment with GILENYA.
- eye problems, especially an inflammation of the eye called uveitis.
- diabetes.
- breathing problems, including during your sleep.
- liver problems.
- high blood pressure.
- any type of skin cancer, including basal cell carcinoma (BCC), melanoma, or squamous cell carcinoma (SCC).
- are pregnant or plan to become pregnant. GILENYA may harm your unborn baby. Talk to your healthcare provider if you are pregnant or are planning to become pregnant. Tell your healthcare provider right away if you become pregnant while taking GILENYA or if you become pregnant within 2 months after you stop taking GILENYA.
  - You should stop taking GILENYA 2 months before trying to become pregnant.
  - If you are a female who can become pregnant, you should use effective birth control during your treatment with GILENYA and for at least 2 months after you stop taking GILENYA.
- are breastfeeding or plan to breastfeed. It is not known if GILENYA passes into your breast milk. Talk to your healthcare provider about the best way to feed your baby if you take GILENYA.

Tell your healthcare provider about all the medicines you take or have recently taken, including prescription and over-the-counter medicines, vitamins, and herbal supplements.
Especially tell your healthcare provider if you take medicines that affect your immune system, including corticosteroids, or have taken them in the past.
Know the medicines you take. Keep a list of your medicines with you to show your healthcare provider and pharmacist when you get a new medicine.
Using GILENYA and other medicines together may affect each other causing serious side effects.

How should I take GILENYA?

- Adults and children will be observed by a healthcare professional for at least 6 hours after taking their first dose of GILENYA. Children should also be observed by a healthcare professional for at least 6 hours after taking their first dose of 0.5 mg of GILENYA when switching from the 0.25 mg dose. See “What is the most important information I should know about GILENYA?”
- Take GILENYA exactly as your healthcare provider tells you to take it.
- Take GILENYA 1 time each day.
- If you take too much GILENYA, call your healthcare provider or go to the nearest hospital emergency room right away.
- Take GILENYA with or without food.
- Do not stop taking GILENYA without talking with your healthcare provider first.
- Call your healthcare provider right away if you miss a dose of GILENYA. You may need to be observed by a healthcare professional for at least 6 hours when you take your next dose. If you need to be observed by a healthcare professional when you take your next dose of GILENYA you will have:
  - an ECG before you take your dose
  - hourly pulse and blood pressure measurements after you take the dose
  - an ECG 6 hours after your dose
- If you have certain types of heart problems, or if you are taking certain types of medicines that can affect your heart, you will be observed overnight by a healthcare professional in a medical facility after you take your dose of GILENYA.
- If you have serious side effects after taking a dose of GILENYA, especially those that require treatment with other medicines, you will stay in the medical facility to be observed overnight. If you were observed overnight, you will also be observed for any serious side effects for at least 6 hours after you take your second dose of GILENYA.

See “What is the most important information I should know about GILENYA?”

What are possible side effects of GILENYA?
GILENYA can cause serious side effects, including:

- See “What is the most important information I should know about GILENYA?”
- swelling and narrowing of the blood vessels in your brain. A condition called PRES (Posterior Reversible Encephalopathy Syndrome) has happened rarely in adults taking GILENYA. Symptoms of PRES usually get better when you stop taking GILENYA. However, if left untreated, it may lead to a stroke. Call your healthcare provider right away if you have any of the following symptoms:

◦ sudden severe headache
◦ sudden confusion

◦ sudden loss of vision or other changes in your vision
◦ seizure

- liver damage. GILENYA may cause liver damage. Your healthcare provider should do blood tests to check your liver before you start taking GILENYA and periodically during treatment. Call your healthcare provider right away if you have any of the following symptoms of liver damage:

◦ nausea
◦ vomiting
◦ stomach pain
◦ tiredness

◦ loss of appetite
◦ your skin or the whites of your eyes turn yellow
◦ dark urine

- breathing problems. Some people who take GILENYA have shortness of breath. Call your healthcare provider right away if you have new or worsening breathing problems.
- severe worsening of multiple sclerosis after stopping GILENYA. When GILENYA is stopped, symptoms of MS can return and become worse compared to before or during treatment. Many people who have worsening of MS symptoms after stopping GILENYA do not return to the level of function that they had before stopping GILENYA. This worsening happens most often within 12 weeks after stopping GILENYA but can happen later. Always talk to your healthcare provider before you stop taking GILENYA for any reason. Tell your healthcare provider if you have worsening symptoms of MS after stopping GILENYA.
- increased blood pressure. Your healthcare provider should check your blood pressure during treatment with GILENYA.
- types of skin cancer, including basal cell carcinoma, melanoma, and squamous cell carcinoma. Tell your healthcare provider if you have any changes in the appearance of your skin, including changes in a mole, a new darkened area on your skin, a sore that does not heal, or growths on your skin, such as a bump that may be shiny, pearly white, skin-colored, or pink. Your healthcare provider should check your skin for any changes at the start of and during treatment with GILENYA. Limit the amount of time you spend in sunlight and ultraviolet (UV) light. Wear protective clothing and use a sunscreen with a high sun protection factor.
- allergic reactions. Call your healthcare provider if you have symptoms of an allergic reaction, including a rash, itchy hives, or swelling of the lips, tongue or face.

The most common side effects of GILENYA include:

- headache
- abnormal liver tests
- diarrhea
- cough
- flu

- inflammation of the sinuses (sinusitis)
- back pain
- stomach-area (abdominal) pain
- pain in arms or legs

Tell your healthcare provider if you have any side effect that bothers you or that does not go away.

These are not all of the possible side effects of GILENYA. For more information, ask your healthcare provider or pharmacist. Call your doctor for medical advice about side effects. You may report side effects to FDA at 1-800-FDA-1088.

How should I store GILENYA?

- Store GILENYA in the original bottle or blister pack in a dry place.
- Store GILENYA at room temperature between 68°F to 77°F (20°C to 25°C).
- Keep GILENYA and all medicines out of the reach of children.

General information about the safe and effective use of GILENYA.

Medicines are sometimes prescribed for purposes other than those listed in a Medication Guide. Do not use GILENYA for a condition for which it was not prescribed. Do not give GILENYA to other people, even if they have the same symptoms that you have. It may harm them. This Medication Guide summarizes the most important information about GILENYA. If you would like more information, talk with your healthcare provider. You can ask your healthcare provider or pharmacist for information about GILENYA that is written for health professionals.

What are the ingredients in GILENYA?

0.25 mg capsules
Active ingredient: fingolimod
Inactive ingredients: gelatin, hydroxypropylbetadex, hydroxypropylcellulose, magnesium stearate, mannitol, titanium dioxide, yellow iron oxide.
0.5 mg capsules
Active ingredient: fingolimod hydrochloride
Inactive ingredients: gelatin, magnesium stearate, mannitol, titanium dioxide, yellow iron oxide.

GILENYA is a registered trademark of Novartis, AG.
Distributed by: Novartis Pharmaceuticals Corporation, East Hanover, New Jersey 07936

© Novartis

This Medication Guide has been approved by the U.S. Food and Drug Administration.

Revised: August 2025

T2025-54

PRINCIPAL DISPLAY PANEL

NDC 0078-0607-15 Rx only

GILENYA®

(fingolimod)

capsules

0.5 mg

Equivalent to 0.56 mg
fingolimod hydrochloride

30 Capsules

Dispense with enclosed Medication Guide.

NOVARTIS

PRINCIPAL DISPLAY PANEL

NDC 0078-0965-89

GILENYA®

(fingolimod)

capsules

0.25 mg

Equivalent to 0.28 mg
fingolimod hydrochloride

7 Capsules

Rx only

This package includes a 1-week supply of capsules.

Dispense with enclosed Medication Guide.

NOVARTIS